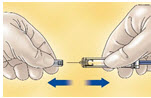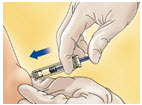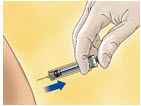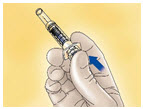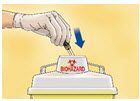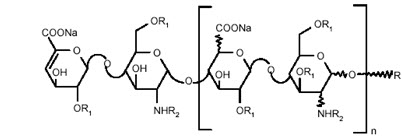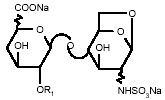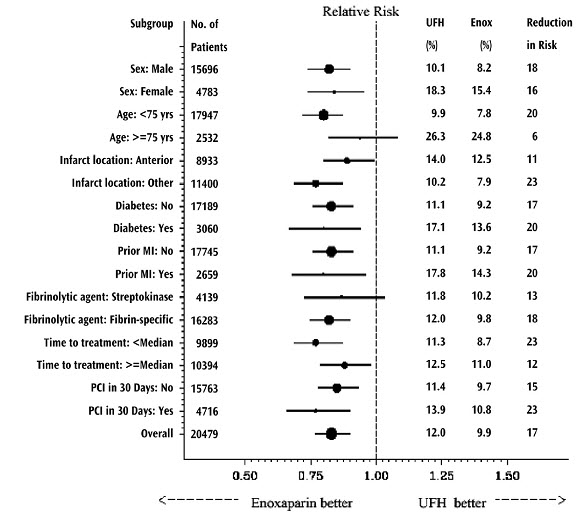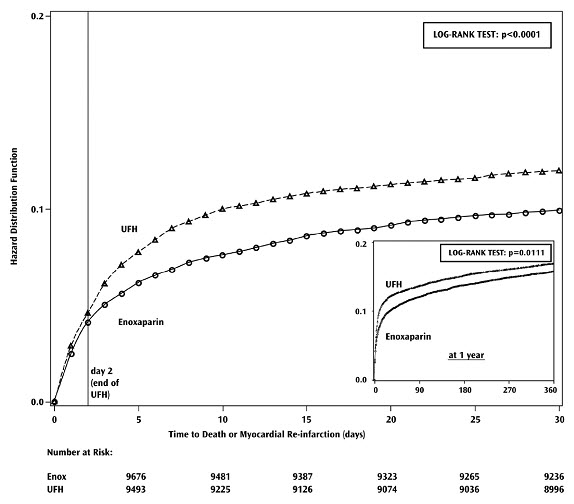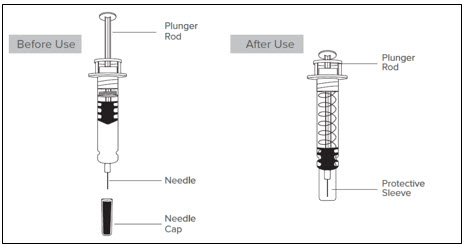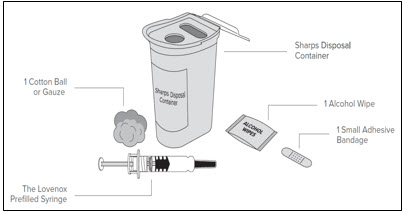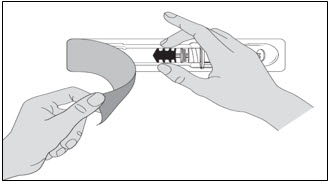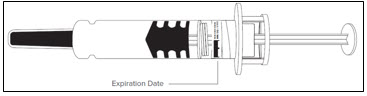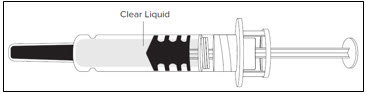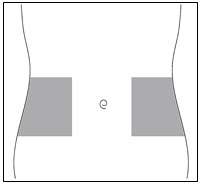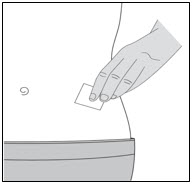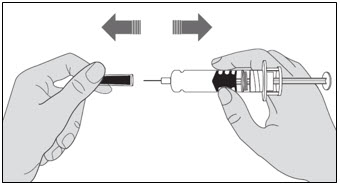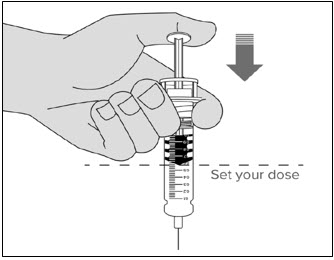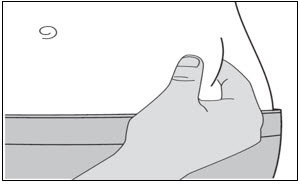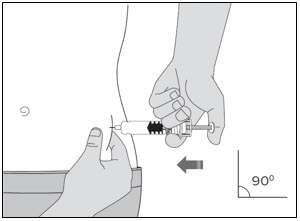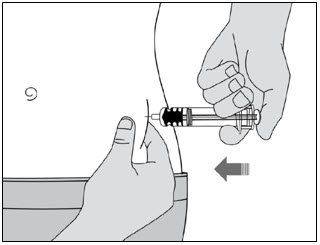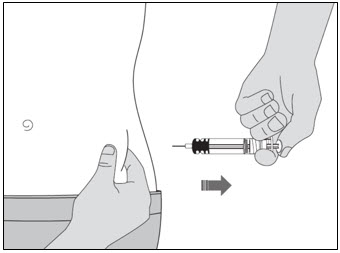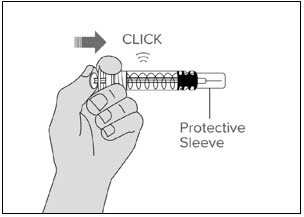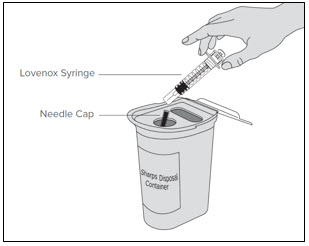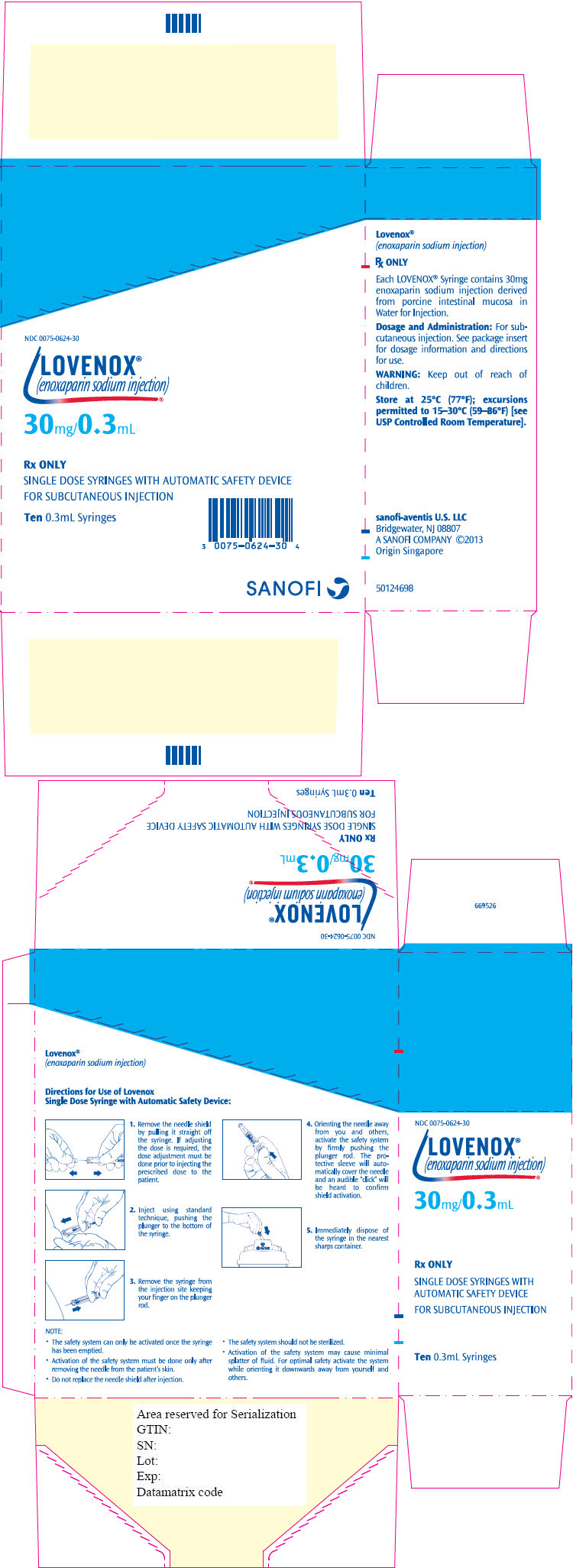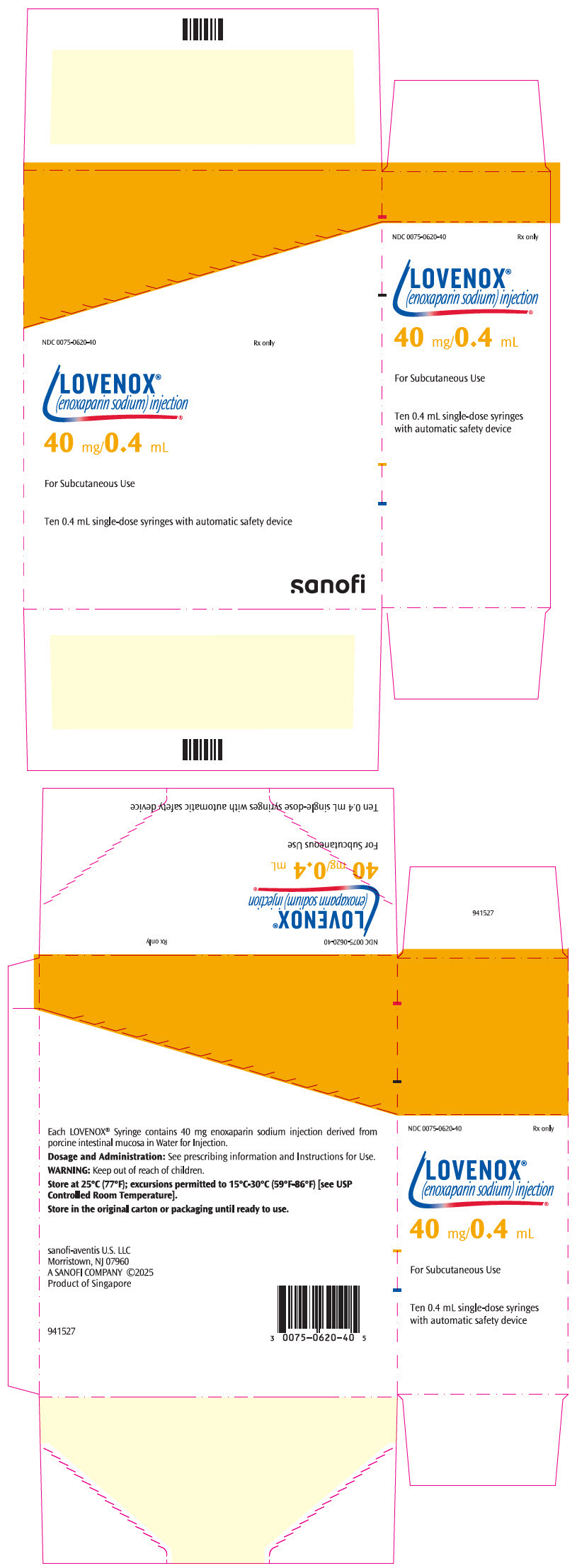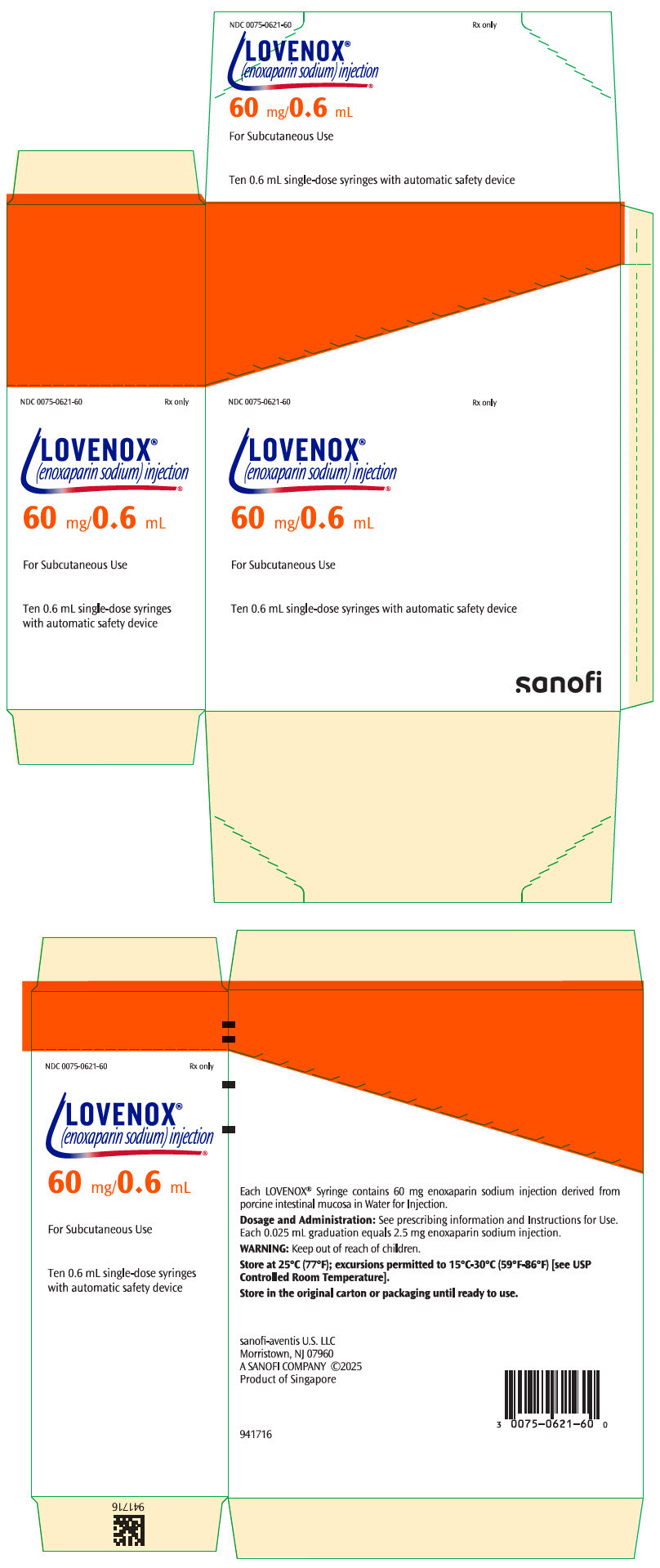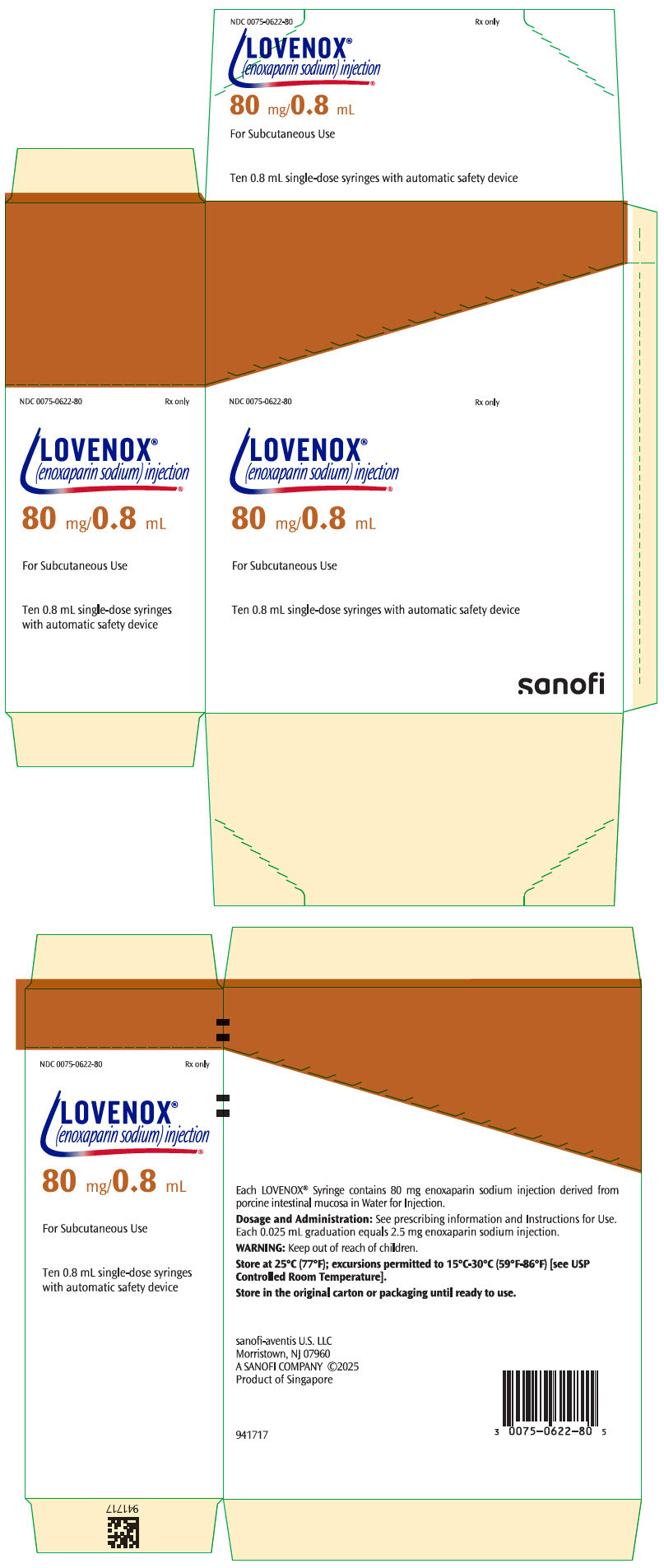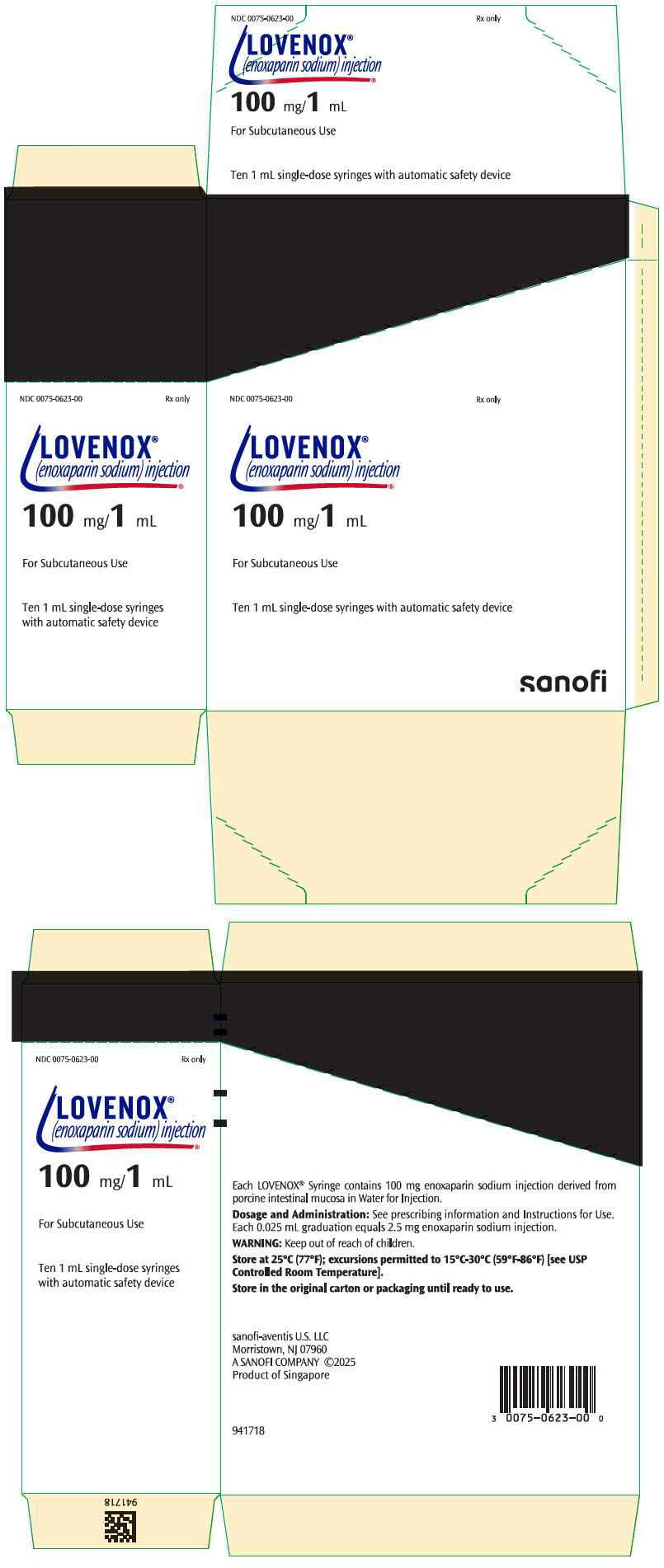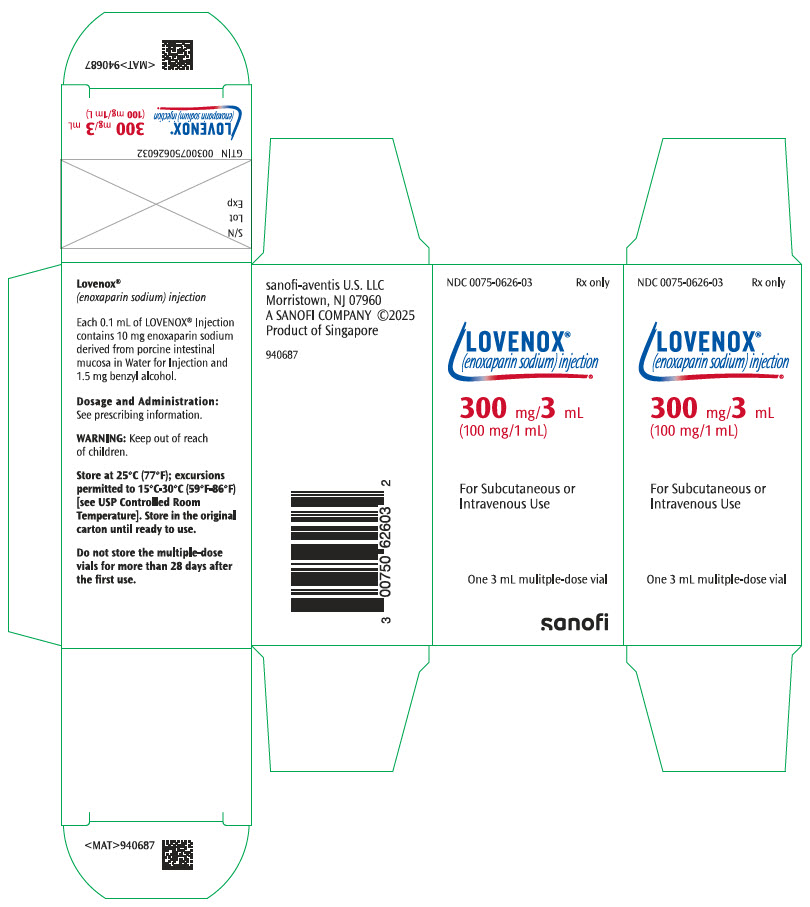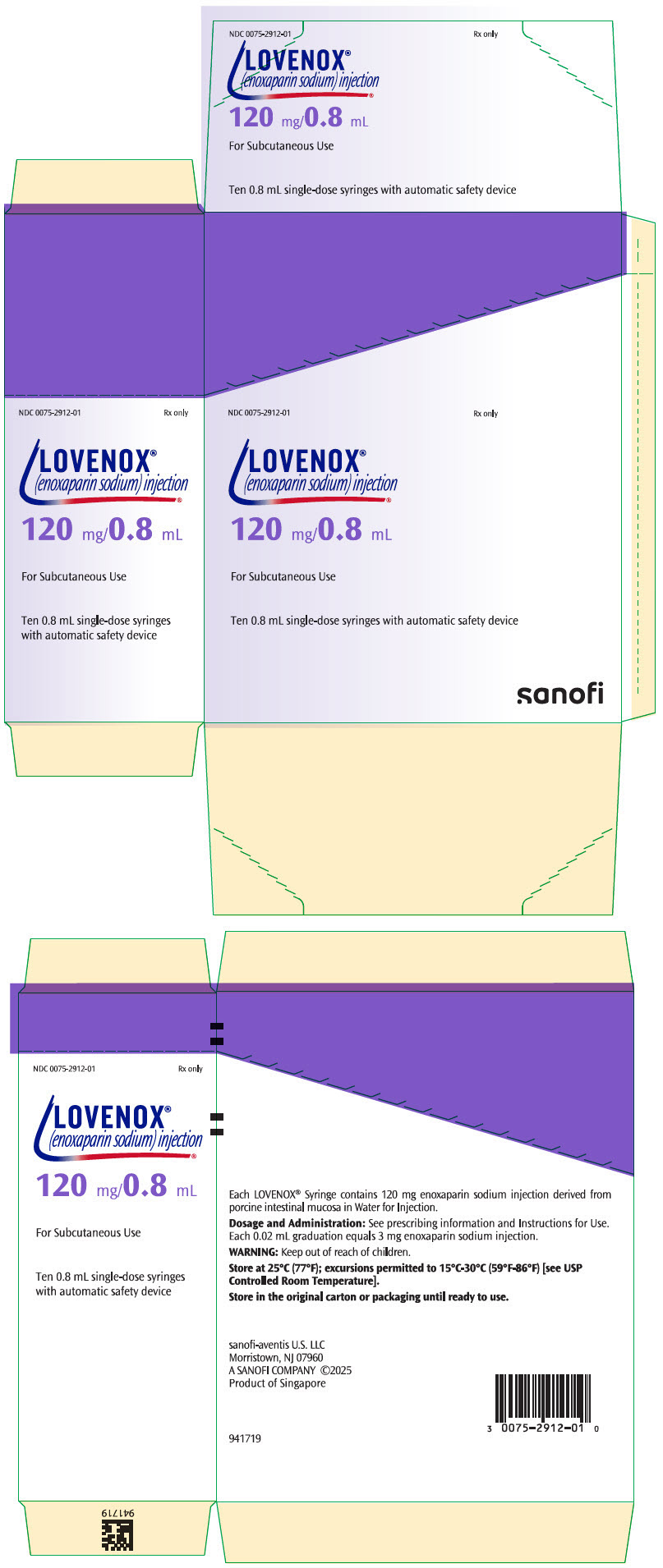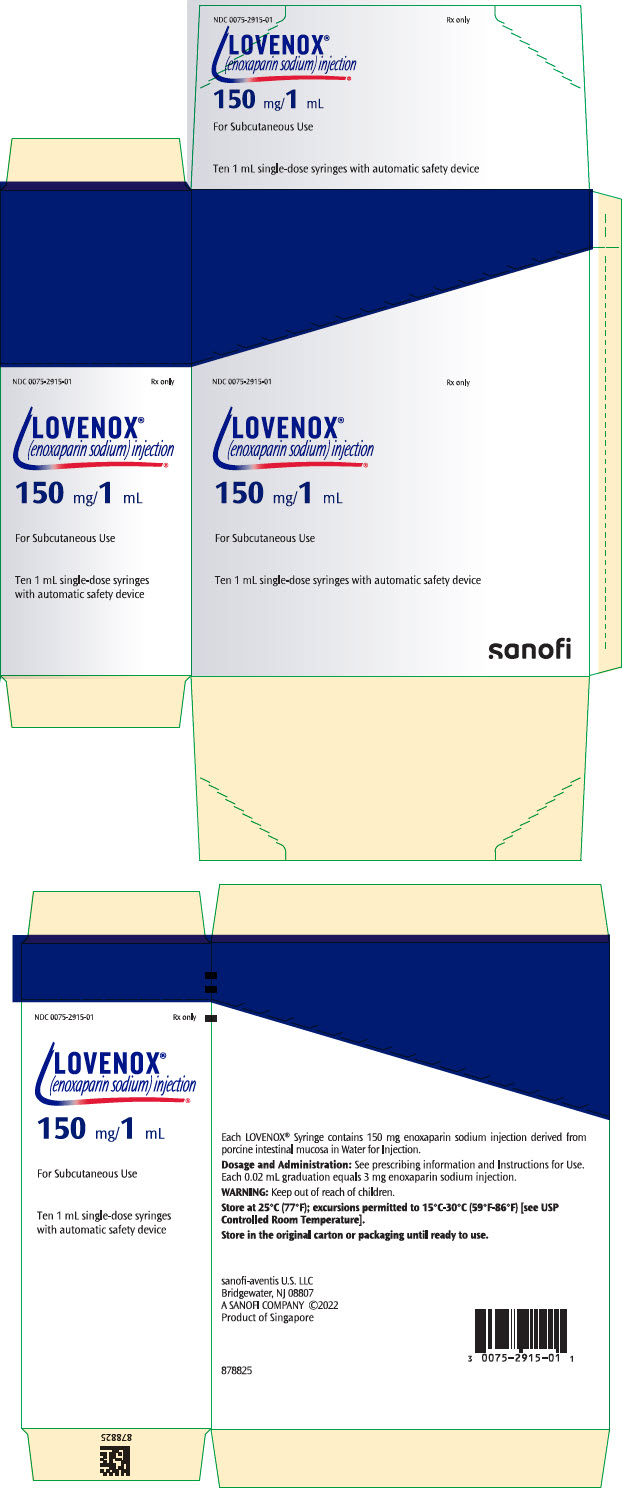 DRUG LABEL: Lovenox
NDC: 0075-0624 | Form: INJECTION
Manufacturer: Sanofi-Aventis U.S. LLC
Category: prescription | Type: HUMAN PRESCRIPTION DRUG LABEL
Date: 20260209

ACTIVE INGREDIENTS: ENOXAPARIN SODIUM 30 mg/0.3 mL
INACTIVE INGREDIENTS: WATER

HIGHLIGHTS OF PRESCRIBING INFORMATION

These highlights do not include all the information needed to use LOVENOX safely and effectively. See full prescribing information for LOVENOX.
LOVENOX (enoxaparin sodium) injection, for subcutaneous and intravenous use
Initial U.S. Approval: 1993

WARNING: SPINAL/EPIDURAL HEMATOMAS

See full prescribing information for complete boxed warning.

Epidural or spinal hematomas may occur in patients who are anticoagulated with low molecular weight heparins (LMWH) or heparinoids and are receiving neuraxial anesthesia or undergoing spinal puncture. These hematomas may result in long-term or permanent paralysis. Consider these risks when scheduling patients for spinal procedures. Factors that can increase the risk of developing epidural or spinal hematomas in these patients include:

- Use of indwelling epidural catheters
- Concomitant use of other drugs that affect hemostasis, such as non-steroidal anti-inflammatory drugs (NSAIDs), platelet inhibitors, and other anticoagulants
- A history of traumatic or repeated epidural or spinal punctures
- A history of spinal deformity or spinal surgery
- Optimal timing between the administration of Lovenox and neuraxial procedures is not known

Monitor patients frequently for signs and symptoms of neurological impairment. If neurological compromise is noted, urgent treatment is necessary. (5.1, 7)

1 INDICATIONS AND USAGE

Lovenox is a low molecular weight heparin (LMWH) indicated for:

- Prophylaxis of deep vein thrombosis (DVT) in abdominal surgery, hip replacement surgery, knee replacement surgery, or medical patients with severely restricted mobility during acute illness (1.1)
- Inpatient treatment of acute DVT with or without pulmonary embolism (1.2)
- Outpatient treatment of acute DVT without pulmonary embolism (1.2)
- Prophylaxis of ischemic complications of unstable angina and non–Q-wave myocardial infarction (MI) (1.3)
- Treatment of acute ST-segment elevation myocardial infarction (STEMI) managed medically or with subsequent percutaneous coronary intervention (PCI) (1.4)

2 DOSAGE AND ADMINISTRATION

See full prescribing information for dosing and administration information. (2)

3 DOSAGE FORMS AND STRENGTHS

100 mg/mL concentration (3):

- Single-dose prefilled syringes: 30 mg/0.3 mL, 40 mg/0.4 mL
- Single-dose graduated prefilled syringes: 60 mg/0.6 mL, 80 mg/0.8 mL, 100 mg/1 mL
- Multiple-dose vial: 300 mg/3 mL

150 mg/mL concentration (3):

- Single-dose graduated prefilled syringes: 120 mg/0.8 mL, 150 mg/1 mL

4 CONTRAINDICATIONS

- Active major bleeding (4)
- History of heparin-induced thrombocytopenia (HIT) within the past 100 days or in the presence of circulating antibodies (4)
- Hypersensitivity to enoxaparin sodium (4)
- Hypersensitivity to heparin or pork products (4)
- Hypersensitivity to benzyl alcohol (for multiple-dose formulation only) (4)

5 WARNINGS AND PRECAUTIONS

- Increased Risk of Hemorrhage: Monitor for signs of bleeding. (5.1, 5.2, 5.3)
- Risk of Heparin-Induced Thrombocytopenia with or without Thrombosis. (5.4)
- Thrombocytopenia: Monitor platelet count closely. (5.5)
- Interchangeability with other heparins: Do not exchange with heparin or other LMWHs. (5.6)
- Increased Risk of Thrombosis in Pregnant Women with Mechanical Prosthetic Heart Valves: Women and their fetuses may be at increased risk. Monitor more frequently and adjust dosage as needed. (5.7)

6 ADVERSE REACTIONS

Most common adverse reactions (>1%) were bleeding, anemia, thrombocytopenia, elevation of serum aminotransferase, diarrhea, nausea, ecchymosis, fever, edema, peripheral edema, dyspnea, confusion, and injection site pain. (6.1)

To report SUSPECTED ADVERSE REACTIONS, contact sanofi-aventis at 1-800-633-1610 or FDA at 1-800-FDA-1088 or www.fda.gov/medwatch.

7 DRUG INTERACTIONS

Discontinue agents which may enhance hemorrhage risk prior to initiation of Lovenox or conduct close clinical and laboratory monitoring. (2.6, 7)

8 USE IN SPECIFIC POPULATIONS

- Severe Renal Impairment: Adjust dose for patients with creatinine clearance <30 mL/min. (2.3, 8.7)
- Geriatric Patients: Monitor for increased risk of bleeding. (8.5)
- Low-Weight Patients: Observe for signs of bleeding. (8.8)

FULL PRESCRIBING INFORMATION

WARNING: SPINAL/EPIDURAL HEMATOMAS

Epidural or spinal hematomas may occur in patients who are anticoagulated with low molecular weight heparins (LMWH) or heparinoids and are receiving neuraxial anesthesia or undergoing spinal puncture. These hematomas may result in long-term or permanent paralysis. Consider these risks when scheduling patients for spinal procedures. Factors that can increase the risk of developing epidural or spinal hematomas in these patients include:

- Use of indwelling epidural catheters
- Concomitant use of other drugs that affect hemostasis, such as non-steroidal anti-inflammatory drugs (NSAIDs), platelet inhibitors, and other anticoagulants
- A history of traumatic or repeated epidural or spinal punctures
- A history of spinal deformity or spinal surgery
- Optimal timing between the administration of Lovenox and neuraxial procedures is not known

Monitor patients frequently for signs and symptoms of neurological impairment. If neurological compromise is noted, urgent treatment is necessary.

Consider the benefits and risks before neuraxial intervention in patients anticoagulated or to be anticoagulated for thromboprophylaxis [see Warnings and Precautions (5.1) and Drug Interactions (7)].

1 INDICATIONS AND USAGE

1.1 Prophylaxis of Deep Vein Thrombosis

Lovenox® is indicated for the prophylaxis of deep vein thrombosis (DVT), which may lead to pulmonary embolism (PE):

- in patients undergoing abdominal surgery who are at risk for thromboembolic complications [see Clinical Studies (14.1)]
- in patients undergoing hip replacement surgery, during and following hospitalization
- in patients undergoing knee replacement surgery
- in medical patients who are at risk for thromboembolic complications due to severely restricted mobility during acute illness

1.2 Treatment of Acute Deep Vein Thrombosis

Lovenox is indicated for:

- the inpatient treatment of acute deep vein thrombosis with or without pulmonary embolism, when administered in conjunction with warfarin sodium
- the outpatient treatment of acute deep vein thrombosis without pulmonary embolism, when administered in conjunction with warfarin sodium

1.3 Prophylaxis of Ischemic Complications of Unstable Angina and Non–Q-Wave Myocardial Infarction

Lovenox is indicated for the prophylaxis of ischemic complications of unstable angina and non–Q-wave myocardial infarction, when concurrently administered with aspirin.

1.4 Treatment of Acute ST-Segment Elevation Myocardial Infarction

Lovenox, when administered concurrently with aspirin, has been shown to reduce the rate of the combined endpoint of recurrent myocardial infarction or death in patients with acute ST-segment elevation myocardial infarction (STEMI) receiving thrombolysis and being managed medically or with percutaneous coronary intervention (PCI).

2 DOSAGE AND ADMINISTRATION

2.1 Pretreatment Evaluation

Evaluate all patients for a bleeding disorder before starting Lovenox treatment, unless treatment is urgently needed.

2.2 Adult Dosage

Abdominal Surgery

The recommended dose of Lovenox is 40 mg by subcutaneous injection once a day (with the initial dose given 2 hours prior to surgery) in patients undergoing abdominal surgery who are at risk for thromboembolic complications. The usual duration of administration is 7 to 10 days [see Clinical Studies (14.1)].

Hip or Knee Replacement Surgery

The recommended dose of Lovenox is 30 mg every 12 hours administered by subcutaneous injection in patients undergoing hip or knee replacement surgery. Administer the initial dose 12 to 24 hours after surgery, provided that hemostasis has been established. The usual duration of administration is 7 to 10 days [see Clinical Studies (14.2)].

A dose of Lovenox of 40 mg once a day subcutaneously may be considered for hip replacement surgery for up to 3 weeks. Administer the initial dose 12 (±3) hours prior to surgery.

Medical Patients during Acute Illness

The recommended dose of Lovenox is 40 mg once a day administered by subcutaneous injection for medical patients at risk for thromboembolic complications due to severely restricted mobility during acute illness. The usual duration of administration is 6 to 11 days [see Clinical Studies (14.3)].

Treatment of Deep Vein Thrombosis with or without Pulmonary Embolism

The recommended dose of Lovenox is 1 mg/kg every 12 hours administered subcutaneously in patients with acute deep vein thrombosis without pulmonary embolism, who can be treated at home in an outpatient setting.

The recommended dose of Lovenox is 1 mg/kg every 12 hours administered subcutaneously or 1.5 mg/kg once a day administered subcutaneously at the same time every day for inpatient (hospital) treatment of patients with acute deep vein thrombosis with pulmonary embolism or patients with acute deep vein thrombosis without pulmonary embolism (who are not candidates for outpatient treatment).

In both outpatient and inpatient (hospital) treatments, initiate warfarin sodium therapy when appropriate (usually within 72 hours of Lovenox). Continue Lovenox for a minimum of 5 days and until a therapeutic oral anticoagulant effect has been achieved (International Normalization Ratio 2 to 3). The average duration of administration is 7 days [see Clinical Studies (14.4)].

Unstable Angina and Non–Q-Wave Myocardial Infarction

The recommended dose of Lovenox is 1 mg/kg administered subcutaneously every 12 hours in conjunction with oral aspirin therapy (100 to 325 mg once daily) in patients with unstable angina or non–Q-wave myocardial infarction. Treat with Lovenox for a minimum of 2 days and continue until clinical stabilization. The usual duration of treatment is 2 to 8 days [see Warnings and Precautions (5.2) and Clinical Studies (14.5)].

Treatment of Acute ST-Segment Elevation Myocardial Infarction

The recommended dose of Lovenox is a single intravenous bolus of 30 mg plus a 1 mg/kg subcutaneous dose followed by 1 mg/kg administered subcutaneously every 12 hours (maximum 100 mg for the first two doses only, followed by 1 mg/kg dosing for the remaining doses) in patients with acute ST-segment elevation myocardial infarction. Reduce the dosage in patients ≥75 years of age [see Dosage and Administration (2.4)]. Unless contraindicated, administer aspirin to all patients as soon as they are identified as having STEMI and continue dosing with 75 to 325 mg once daily.

When administered in conjunction with a thrombolytic (fibrin specific or non–fibrin specific), administer Lovenox between 15 minutes before and 30 minutes after the start of fibrinolytic therapy. The usual duration of Lovenox therapy is 8 days or until hospital discharge.

For patients managed with percutaneous coronary intervention (PCI), if the last Lovenox subcutaneous administration was given less than 8 hours before balloon inflation, no additional dosing is needed. If the last Lovenox subcutaneous administration was given more than 8 hours before balloon inflation, administer an intravenous bolus of 0.3 mg/kg of Lovenox [see Warnings and Precautions (5.2)].

2.3 Dose Reduction for Patients with Severe Renal Impairment

The recommended prophylaxis and treatment dosage regimens for patients with severe renal impairment (creatinine clearance <30 mL/min) are described in Table 1 [see Use in Specific Populations (8.7) and Clinical Pharmacology (12.3)].

Table 1: Dosage Regimens for Patients with Severe Renal Impairment (creatinine clearance <30 mL/minute)
Indication | Dosage Regimen
Prophylaxis in abdominal surgery | 30 mg administered subcutaneously once daily
Prophylaxis in hip or knee replacement surgery | 30 mg administered subcutaneously once daily
Prophylaxis in medical patients during acute illness | 30 mg administered subcutaneously once daily
Inpatient treatment of acute deep vein thrombosis with or without pulmonary embolism, when administered in conjunction with warfarin sodium | 1 mg/kg administered subcutaneously once daily
Outpatient treatment of acute deep vein thrombosis without pulmonary embolism, when administered in conjunction with warfarin sodium | 1 mg/kg administered subcutaneously once daily
Prophylaxis of ischemic complications of unstable angina and non–Q-wave myocardial infarction, when concurrently administered with aspirin | 1 mg/kg administered subcutaneously once daily
Treatment of acute ST-segment elevation myocardial infarction in patients <75 years of age, when administered in conjunction with aspirin | 30 mg single intravenous bolus plus a 1 mg/kg subcutaneous dose followed by 1 mg/kg administered subcutaneously once daily
Treatment of acute ST-segment elevation myocardial infarction in geriatric patients ≥75 years of age, when administered in conjunction with aspirin | 1 mg/kg administered subcutaneously once daily (no initial bolus)

Although no dose adjustment is recommended in patients with creatinine clearance 30 to 50 mL/min and creatinine clearance 50 to 80 mL/min, observe these patients frequently for signs and symptoms of bleeding.

2.4 Recommended Dosage for Geriatric Patients with Acute ST-Segment Elevation Myocardial Infarction

For treatment of acute ST-segment elevation myocardial infarction in geriatric patients ≥75 years of age, do not use an initial intravenous bolus. Initiate dosing with 0.75 mg/kg subcutaneously every 12 hours (maximum 75 mg for the first two doses only, followed by 0.75 mg/kg dosing for the remaining doses) [see Use in Specific Populations (8.5) and Clinical Pharmacology (12.3)].

No dose adjustment is necessary for other indications in geriatric patients unless kidney function is impaired [see Dosage and Administration (2.2)].

2.5 Administration

Do not administer Lovenox by intramuscular injection.

Administer Lovenox by intravenous or subcutaneous injection only.

Lovenox is a clear, colorless to pale yellow sterile solution, and as with other parenteral drug products, should be inspected visually for particulate matter and discoloration prior to administration.

Use a tuberculin syringe or equivalent when using Lovenox multiple-dose vials to assure withdrawal of the appropriate volume of drug.

Patients may self-inject by the subcutaneous route of administration only after their physicians determine that it is appropriate and with medical follow-up, as necessary. Provide proper training in subcutaneous injection technique before allowing self-injection (with or without the assistance of an injection device).

Subcutaneous Injection Technique

- Position patients in a supine position for Lovenox administration by deep subcutaneous injection.
- Do not expel the air bubble from the prefilled syringes before the injection, to avoid the loss of drug.
- Do not inject into skin that has bruises or scars. Do not inject through clothes.
- Alternate injection sites between the left and right anterolateral and left and right posterolateral abdominal wall.
- Introduce the whole length of the needle into a skin fold held between the thumb and forefinger; hold the skin fold throughout the injection. To minimize bruising, do not rub the injection site after completion of the injection.

Lovenox prefilled syringes and graduated prefilled syringes are for single, one-time use only and are available with a system that shields the needle after injection.

Remove the prefilled syringe from the packaging by peeling at the arrow as directed on the lid. Do not remove by pulling on the plunger as this may damage the syringe.

1. Remove the needle shield by pulling it straight off the syringe (see Figure A). If less than the full syringe volume is needed to administer the prescribed dose, eject syringe contents until the prescribed dose is left in the syringe.
  Figure A
2. Inject using standard technique, pushing the plunger to the bottom of the syringe (see Figure B).
  Figure B
3. Remove the syringe from the injection site keeping your finger on the plunger rod (see Figure C).
  Figure C
4. Orient the needle away from you and others, and activate the safety system by firmly pushing the plunger rod. The protective sleeve will automatically cover the needle and an audible "click" will be heard to confirm shield activation (see Figure D).
  Figure D
5. Immediately dispose of the syringe in the nearest sharps container (see Figure E).
  Figure E

NOTE:

- The safety system can only be activated once the syringe has been emptied.
- Activation of the safety system must be done only after removing the needle from the patient's skin.
- Do not replace the needle shield after injection.
- The safety system should not be sterilized.

Activation of the safety system may cause minimal splatter of fluid. For optimal safety, activate the system while orienting it downwards away from yourself and others.

Intravenous (Bolus) Injection Technique

Use the multiple-dose vial for intravenous injections. Administer Lovenox through an intravenous line. Do not mix or coadminister Lovenox with other medications. Flush the intravenous access device with a sufficient volume of saline or dextrose solution prior to and following the intravenous bolus administration of Lovenox, to prevent mixing of drugs. Lovenox is compatible with normal saline solution (0.9%) or 5% dextrose in water.

2.6 Monitoring for Safety

During therapy monitor complete blood counts including platelets and stool occult blood.

Assess for signs and symptoms of bleeding.

In patients with renal impairment anti-Factor Xa levels may be used to monitor the anticoagulant effects of Lovenox.

If during Lovenox therapy abnormal coagulation parameters or bleeding should occur, anti-Factor Xa levels may be used to monitor the anticoagulant effects of Lovenox [see Clinical Pharmacology (12.3)].

Prothrombin Time (PT) and Activated Partial Thromboplastin Time (aPTT) are not adequate for monitoring the anticoagulant effects of Lovenox.

3 DOSAGE FORMS AND STRENGTHS

Lovenox is a clear, colorless to pale-yellow solution available in two concentrations.

 | 100 mg/mL Concentration
 | – Single-Dose Prefilled Syringes | 30 mg/0.3 mL, 40 mg/0.4 mL
 | – Single-Dose Graduated Prefilled Syringes | 60 mg/0.6 mL, 80 mg/0.8 mL, 100 mg/1 mL
 | – Multiple-Dose Vial | 300 mg/3 mL
 | 150 mg/mL Concentration
 | – Single-Dose Graduated Prefilled Syringes | 120 mg/0.8 mL, 150 mg/1 mL

4 CONTRAINDICATIONS

Lovenox is contraindicated in patients with:

- Active major bleeding
- History of immune-mediated heparin-induced thrombocytopenia (HIT) within the past 100 days or in the presence of circulating antibodies [see Warnings and Precautions (5.4)]
- Known hypersensitivity to enoxaparin sodium (e.g., pruritus, urticaria, anaphylactic/anaphylactoid reactions) [see Adverse Reactions (6.2)]
- Known hypersensitivity to heparin or pork products
- Known hypersensitivity to benzyl alcohol (which is in only the multiple-dose formulation of Lovenox) [see Warnings and Precautions (5.8)]

5 WARNINGS AND PRECAUTIONS

5.1 Increased Risk of Hemorrhage

Cases of epidural or spinal hemorrhage and subsequent hematomas have been reported with the use of Lovenox and epidural or spinal anesthesia/analgesia or spinal puncture procedures, resulting in long-term or permanent paralysis. The risk of these events is higher with the use of postoperative indwelling epidural catheters, with the concomitant use of additional drugs affecting hemostasis such as NSAIDs, with traumatic or repeated epidural or spinal puncture, or in patients with a history of spinal surgery or spinal deformity [see Boxed Warning, Adverse Reactions (6.2) and Drug Interactions (7)].

To reduce the potential risk of bleeding associated with the concurrent use of Lovenox and epidural or spinal anesthesia/analgesia or spinal puncture, consider the pharmacokinetic profile of Lovenox [see Clinical Pharmacology (12.3)]. Placement or removal of an epidural catheter or lumbar puncture is best performed when the anticoagulant effect of Lovenox is low; however, the exact timing to reach a sufficiently low anticoagulant effect in each patient is not known.

Placement or removal of a catheter should be delayed for at least 12 hours after administration of lower doses (30 mg once or twice daily or 40 mg once daily) of Lovenox and at least 24 hours after the administration of higher doses (0.75 mg/kg twice daily, 1 mg/kg twice daily, or 1.5 mg/kg once daily) of Lovenox. Anti-Xa levels are still detectable at these time points, and these delays are not a guarantee that neuraxial hematoma will be avoided. Patients receiving the 0.75 mg/kg twice-daily dose or the 1 mg/kg twice-daily dose should not receive the second Lovenox dose in the twice-daily regimen to allow a longer delay before catheter placement or removal. Likewise, although a specific recommendation for timing of a subsequent Lovenox dose after catheter removal cannot be made, consider delaying this next dose for at least four hours, based on a benefit-risk assessment considering both the risk for thrombosis and the risk for bleeding in the context of the procedure and patient risk factors. For patients with creatinine clearance <30 mL/minute, additional considerations are necessary because elimination of Lovenox is more prolonged; consider doubling the timing of removal of a catheter, at least 24 hours for the lower prescribed dose of Lovenox (30 mg once daily) and at least 48 hours for the higher dose (1 mg/kg/day) [see Clinical Pharmacology (12.3)].

Should the physician decide to administer anticoagulation in the context of epidural or spinal anesthesia/analgesia or lumbar puncture, frequent monitoring must be exercised to detect any signs and symptoms of neurological impairment such as midline back pain, sensory and motor deficits (numbness or weakness in lower limbs), and bowel and/or bladder dysfunction. Instruct patients to report immediately if they experience any of the above signs or symptoms. If signs or symptoms of spinal hematoma are suspected, initiate urgent diagnosis and treatment including consideration for spinal cord decompression even though such treatment may not prevent or reverse neurological sequelae.

Use Lovenox with extreme caution in conditions with increased risk of hemorrhage, such as bacterial endocarditis, congenital or acquired bleeding disorders, active ulcerative and angiodysplastic gastrointestinal disease, hemorrhagic stroke, or shortly after brain, spinal, or ophthalmological surgery, or in patients treated concomitantly with platelet inhibitors.

Major hemorrhages including retroperitoneal and intracranial bleeding have been reported. Some of these cases have been fatal.

Bleeding can occur at any site during therapy with Lovenox. An unexplained fall in hematocrit or blood pressure should lead to a search for a bleeding site.

5.2 Increased Risk of Bleeding following Percutaneous Coronary Revascularization Procedures

To minimize the risk of bleeding following the vascular instrumentation during the treatment of unstable angina, non–Q-wave myocardial infarction and acute ST-segment elevation myocardial infarction, adhere precisely to the intervals recommended between Lovenox doses. It is important to achieve hemostasis at the puncture site after PCI. In case a closure device is used, the sheath can be removed immediately. If a manual compression method is used, sheath should be removed 6 hours after the last intravenous/subcutaneous Lovenox. If the treatment with Lovenox is to be continued, the next scheduled dose should be given no sooner than 6 to 8 hours after sheath removal. The site of the procedure should be observed for signs of bleeding or hematoma formation [see Dosage and Administration (2.1)].

5.3 Increased Risk of Bleeding in Patients with Concomitant Medical Conditions

Lovenox should be used with care in patients with a bleeding diathesis, uncontrolled arterial hypertension or a history of recent gastrointestinal ulceration, diabetic retinopathy, renal dysfunction and hemorrhage.

5.4 Risk of Heparin-Induced Thrombocytopenia with or without Thrombosis

Lovenox may cause heparin-induced thrombocytopenia (HIT) or heparin-induced thrombocytopenia with thrombosis (HITTS). HITTS may lead to organ infarction, limb ischemia, or death. Monitor thrombocytopenia of any degree closely.

Use of Lovenox in patients with a history of immune-mediated HIT within the past 100 days or in the presence of circulating antibodies is contraindicated [see Contraindications (4)]. Circulating antibodies may persist for several years.

Only use Lovenox in patients with a history of HIT if more than 100 days have elapsed since the prior HIT episode and no circulating antibodies are present. Because HIT may still occur in these circumstances, the decision to use Lovenox in such a case must be made only after a careful benefit-risk assessment and after non-heparin alternative treatments are considered.

5.5 Thrombocytopenia

Thrombocytopenia can occur with the administration of Lovenox.

Moderate thrombocytopenia (platelet counts between 100,000/mm^3 and 50,000/mm^3) occurred at a rate of 1.3% in patients given Lovenox, 1.2% in patients given heparin, and 0.7% in patients given placebo in clinical trials.

Platelet counts less than 50,000/mm^3 occurred at a rate of 0.1% in patients given Lovenox, in 0.2% of patients given heparin, and 0.4% of patients given placebo in the same trials.

Thrombocytopenia of any degree should be monitored closely. If the platelet count falls below 100,000/mm^3, Lovenox should be discontinued.

5.6 Interchangeability with other Heparins

Lovenox cannot be used interchangeably (unit for unit) with heparin or other low molecular weight heparins as they differ in manufacturing process, molecular weight distribution, anti-Xa and anti-IIa activities, units, and dosage. Each of these medicines has its own instructions for use.

5.7 Increased Risk of Thrombosis in Pregnant Women with Mechanical Prosthetic Heart Valves

Use of Lovenox for thromboprophylaxis in pregnant women with mechanical prosthetic heart valves may result in valve thrombosis. In a clinical study of pregnant women with mechanical prosthetic heart valves given Lovenox (1 mg/kg twice daily) to reduce the risk of thromboembolism, 2 of 8 women developed clots resulting in blockage of the valve and leading to maternal and fetal death. No patients in the heparin/warfarin group (0 of 4 women) died. There also have been isolated postmarketing reports of valve thrombosis in pregnant women with mechanical prosthetic heart valves while receiving Lovenox for thromboprophylaxis. Women with mechanical prosthetic heart valves may be at higher risk for thromboembolism during pregnancy and, when pregnant, have a higher rate of fetal loss from stillbirth, spontaneous abortion, and premature delivery. Therefore, frequent monitoring of peak and trough anti-Factor Xa levels, and adjusting of dosage may be needed [see Use in Specific Populations (8.6)].

5.8 Risk of Serious Adverse Reactions in Infants due to Benzyl Alcohol Preservative

Lovenox multiple-dose vials are not approved for use in neonates or infants.

Serious and fatal adverse reactions including "gasping syndrome" can occur in neonates and low-birth-weight infants treated with benzyl alcohol-preserved drugs, including Lovenox multiple-dose vials. The "gasping syndrome" is characterized by central nervous system depression, metabolic acidosis, and gasping respirations. The minimum amount of benzyl alcohol at which serious adverse reactions may occur is not known (Lovenox multiple-dose vials contain 15 mg of benzyl alcohol per mL) [see Use in Specific Populations (8.4)].

Because benzyl alcohol may cross the placenta, if anticoagulation with Lovenox is needed during pregnancy, use the preservative-free formulations where possible [see Use in Specific Populations (8.1)].

6 ADVERSE REACTIONS

The following serious adverse reactions are also discussed in other sections of the labeling:

- Spinal/epidural hematomas [see Boxed Warning and Warnings and Precautions (5.1)]
- Increased Risk of Hemorrhage [see Warnings and Precautions (5.1)]
- Thrombocytopenia [see Warnings and Precautions (5.5)]

6.1 Clinical Trials Experience

Because clinical trials are conducted under widely varying conditions, adverse reaction rates observed in the clinical trials of a drug cannot be directly compared to rates in the clinical trials of another drug and may not reflect the rates observed in clinical practice.

During clinical development for the approved indications, 15,918 patients were exposed to Lovenox. These included 1,228 for prophylaxis of deep vein thrombosis following abdominal surgery in patients at risk for thromboembolic complications, 1,368 for prophylaxis of deep vein thrombosis following hip or knee replacement surgery, 711 for prophylaxis of deep vein thrombosis in medical patients with severely restricted mobility during acute illness, 1,578 for prophylaxis of ischemic complications in unstable angina and non–Q-wave myocardial infarction, 10,176 for treatment of acute ST-elevation myocardial infarction, and 857 for treatment of deep vein thrombosis with or without pulmonary embolism. Lovenox doses in the clinical trials for prophylaxis of deep vein thrombosis following abdominal or hip or knee replacement surgery or in medical patients with severely restricted mobility during acute illness ranged from 40 mg subcutaneously once daily to 30 mg subcutaneously twice daily. In the clinical studies for prophylaxis of ischemic complications of unstable angina and non–Q-wave myocardial infarction doses were 1 mg/kg every 12 hours and in the clinical studies for treatment of acute ST-segment elevation myocardial infarction Lovenox doses were a 30 mg intravenous bolus followed by 1 mg/kg every 12 hours subcutaneously.

Hemorrhage

The following rates of major bleeding events have been reported during clinical trials with Lovenox (see Tables 2 to 7).

Table 2: Major Bleeding Episodes following Abdominal and Colorectal Surgery [Bleeding complications were considered major: (1) if the hemorrhage caused a significant clinical event, or (2) if accompanied by a hemoglobin decrease ≥2 g/dL or transfusion of 2 or more units of blood products. Retroperitoneal, intraocular, and intracranial hemorrhages were always considered major.]
 | Dosing Regimen
Indications | Lovenox 40 mg daily subcutaneously | Heparin 5000 U q8h subcutaneously
Abdominal Surgery | n=555 23 (4%) | n=560 16 (3%)
Colorectal Surgery | n=673 28 (4%) | n=674 21 (3%)

Table 3: Major Bleeding Episodes following Hip or Knee Replacement Surgery [Bleeding complications were considered major: (1) if the hemorrhage caused a significant clinical event, or (2) if accompanied by a hemoglobin decrease ≥2 g/dL or transfusion of 2 or more units of blood products. Retroperitoneal and intracranial hemorrhages were always considered major. In the knee replacement surgery trials, intraocular hemorrhages were also considered major hemorrhages.]
 | Dosing Regimen
Indications | Lovenox 40 mg daily subcutaneously | Lovenox 30 mg q12h subcutaneously | Heparin 15,000 U/24h subcutaneously
Hip Replacement Surgery without Extended Prophylaxis [Lovenox 30 mg every 12 hours subcutaneously initiated 12 to 24 hours after surgery and continued for up to 14 days after surgery] | – | n=786 31 (4%) | n=541 32 (6%)
Hip Replacement Surgery with Extended Prophylaxis | – | – | –
Peri-operative Period [Lovenox 40 mg subcutaneously once a day initiated up to 12 hours prior to surgery and continued for up to 7 days after surgery] | n=288 4 (2%) | – | –
Extended Prophylaxis Period [Lovenox 40 mg subcutaneously once a day for up to 21 days after discharge] | n=221 0 (0%) | – | –
Knee Replacement Surgery without Extended Prophylaxis | – | n=294 3 (1%) | n=225 3 (1%)

NOTE: At no time point were the 40 mg once a day pre-operative and the 30 mg every 12 hours postoperative hip replacement surgery prophylactic regimens compared in clinical trials. Injection site hematomas during the extended prophylaxis period after hip replacement surgery occurred in 9% of the Lovenox patients versus 1.8% of the placebo patients.

Table 4: Major Bleeding Episodes in Medical Patients with Severely Restricted Mobility during Acute Illness [Bleeding complications were considered major: (1) if the hemorrhage caused a significant clinical event, (2) if the hemorrhage caused a decrease in hemoglobin of ≥2 g/dL or transfusion of 2 or more units of blood products. Retroperitoneal and intracranial hemorrhages were always considered major although none were reported during the trial.]
 | Dosing Regimen
Indication | Lovenox [The rates represent major bleeding on study medication up to 24 hours after last dose.] 20 mg daily subcutaneously | Lovenox 40 mg daily subcutaneously | Placebo
Medical Patients during Acute Illness | n=351 1 (<1%) | n=360 3 (<1%) | n=362 2 (<1%)

Table 5: Major Bleeding Episodes in Deep Vein Thrombosis with or without Pulmonary Embolism Treatment [Bleeding complications were considered major: (1) if the hemorrhage caused a significant clinical event, or (2) if accompanied by a hemoglobin decrease ≥2 g/dL or transfusion of 2 or more units of blood products. Retroperitoneal, intraocular, and intracranial hemorrhages were always considered major.]
 | Dosing Regimen [All patients also received warfarin sodium (dose-adjusted according to PT to achieve an INR of 2.0 to 3.0) commencing within 72 hours of Lovenox or standard heparin therapy and continuing for up to 90 days.]
Indication | Lovenox 1.5 mg/kg daily subcutaneously | Lovenox 1 mg/kg q12h subcutaneously | Heparin aPTT Adjusted Intravenous Therapy
Treatment of DVT and PE | n=298 5 (2%) | n=559 9 (2%) | n=554 9 (2%)

Table 6: Major Bleeding Episodes in Unstable Angina and Non–Q-Wave Myocardial Infarction
 | Dosing Regimen
Indication | Lovenox [The rates represent major bleeding on study medication up to 12 hours after dose.] 1 mg/kg q12h subcutaneously | Heparin aPTT Adjusted Intravenous Therapy
Unstable Angina and Non–Q-Wave MI [Aspirin therapy was administered concurrently (100 to 325 mg per day).] , [Bleeding complications were considered major: (1) if the hemorrhage caused a significant clinical event, or (2) if accompanied by a hemoglobin decrease by ≥3 g/dL or transfusion of 2 or more units of blood products. Intraocular, retroperitoneal, and intracranial hemorrhages were always considered major.] | n=1578 17 (1%) | n=1529 18 (1%)

Table 7: Major Bleeding Episodes in Acute ST-Segment Elevation Myocardial Infarction
 | Dosing Regimen
Indication | Lovenox [The rates represent major bleeding (including ICH) up to 30 days.] Initial 30 mg intravenous bolus followed by 1 mg/kg q12h subcutaneously | Heparin aPTT Adjusted Intravenous Therapy
Acute ST-Segment Elevation Myocardial Infarction | n=10176 n (%) | n=10151 n (%)
Major bleeding (including ICH) [Bleedings were considered major if the hemorrhage caused a significant clinical event associated with a hemoglobin decrease by ≥5 g/dL. ICH were always considered major.] | 211 (2.1) | 138 (1.4)
Intracranial hemorrhages (ICH) | 84 (0.8) | 66 (0.7)

Elevations of Serum Aminotransferases

Asymptomatic increases in aspartate (AST [SGOT]) and alanine (ALT [SGPT]) aminotransferase levels greater than three times the upper limit of normal of the laboratory reference range have been reported in up to 6.1% and 5.9% of patients, respectively, during treatment with Lovenox.

Since aminotransferase determinations are important in the differential diagnosis of myocardial infarction, liver disease, and pulmonary emboli, elevations that might be caused by drugs like Lovenox should be interpreted with caution.

Local Reactions

Local irritation, pain, hematoma, ecchymosis, and erythema may follow subcutaneous injection of Lovenox.

Adverse Reactions in Patients Receiving Lovenox for Prophylaxis or Treatment of DVT, PE

Other adverse reactions that were thought to be possibly or probably related to treatment with Lovenox, heparin, or placebo in clinical trials with patients undergoing hip or knee replacement surgery, abdominal or colorectal surgery, or treatment for DVT and that occurred at a rate of at least 2% in the Lovenox group, are provided below (see Tables 8 to 11).

Table 8: Adverse Reactions Occurring at ≥2% Incidence in Lovenox-Treated Patients Undergoing Abdominal or Colorectal Surgery
 | Dosing Regimen
 | Lovenox 40 mg daily subcutaneously n=1228 % |  | Heparin 5000 U q8h subcutaneously n=1234 %
Adverse Reaction | Severe | Total | Severe | Total
Hemorrhage | <1 | 7 | <1 | 6
Anemia | <1 | 3 | <1 | 3
Ecchymosis | 0 | 3 | 0 | 3

Table 9: Adverse Reactions Occurring at ≥2% Incidence in Lovenox-Treated Patients Undergoing Hip or Knee Replacement Surgery
 | Dosing Regimen
 | Lovenox 40 mg daily subcutaneously |  |  |  | Lovenox 30 mg q12h subcutaneously |  | Heparin 15,000 U/24h subcutaneously |  | Placebo q12h subcutaneously
 | Peri-operative Period |  | Extended Prophylaxis Period
 | n=288 [Data represent Lovenox 40 mg subcutaneously once a day initiated up to 12 hours prior to surgery in 288 hip replacement surgery patients who received Lovenox peri-operatively in an unblinded fashion in one clinical trial.] % |  | n=131 [Data represent Lovenox 40 mg subcutaneously once a day given in a blinded fashion as extended prophylaxis at the end of the peri-operative period in 131 of the original 288 hip replacement surgery patients for up to 21 days in one clinical trial.] % |  | n=1080 % |  | n=766 % |  | n=115 %
Adverse Reaction | Severe | Total | Severe | Total | Severe | Total | Severe | Total | Severe | Total
Fever | 0 | 8 | 0 | 0 | <1 | 5 | <1 | 4 | 0 | 3
Hemorrhage | <1 | 13 | 0 | 5 | <1 | 4 | 1 | 4 | 0 | 3
Nausea | – | – | – |  | <1 | 3 | <1 | 2 | 0 | 2
Anemia | 0 | 16 | 0 | <2 | <1 | 2 | 2 | 5 | <1 | 7
Edema | – | – | – | – | <1 | 2 | <1 | 2 | 0 | 2
Peripheral edema | 0 | 6 | 0 | 0 | <1 | 3 | <1 | 4 | 0 | 3

Table 10: Adverse Reactions Occurring at ≥2% Incidence in Lovenox-Treated Medical Patients with Severely Restricted Mobility during Acute Illness
 | Dosing Regimen
Adverse Reaction | Lovenox 40 mg daily subcutaneously n=360 % | Placebo daily subcutaneously n=362 %
Dyspnea | 3.3 | 5.2
Thrombocytopenia | 2.8 | 2.8
Confusion | 2.2 | 1.1
Diarrhea | 2.2 | 1.7
Nausea | 2.5 | 1.7

Table 11: Adverse Reactions Occurring at ≥2% Incidence in Lovenox-Treated Patients Undergoing Treatment of Deep Vein Thrombosis with or without Pulmonary Embolism
 | Dosing Regimen
 | Lovenox 1.5 mg/kg daily subcutaneously n=298 % |  | Lovenox 1 mg/kg q12h subcutaneously n=559 % |  | Heparin aPTT Adjusted Intravenous Therapy n=544 %
Adverse Reaction | Severe | Total | Severe | Total | Severe | Total
Injection Site Hemorrhage | 0 | 5 | 0 | 3 | <1 | <1
Injection Site Pain | 0 | 2 | 0 | 2 | 0 | 0
Hematuria | 0 | 2 | 0 | <1 | <1 | 2

Adverse Events in Lovenox-Treated Patients with Unstable Angina or Non–Q-Wave Myocardial Infarction

Non-hemorrhagic clinical events reported to be related to Lovenox therapy occurred at an incidence of ≤1%.

Non-major hemorrhagic events, primarily injection site ecchymosis and hematomas, were more frequently reported in patients treated with subcutaneous Lovenox than in patients treated with intravenous heparin.

Serious adverse events with Lovenox or heparin in a clinical trial in patients with unstable angina or non–Q-wave myocardial infarction that occurred at a rate of at least 0.5% in the Lovenox group are provided below (see Table 12).

Table 12: Serious Adverse Events Occurring at ≥0.5% Incidence in Lovenox-Treated Patients with Unstable Angina or Non–Q-Wave Myocardial Infarction
 | Dosing Regimen
 | Lovenox 1 mg/kg q12h subcutaneously | Heparin aPTT Adjusted Intravenous Therapy
Adverse Event | n=1578 n (%) | n=1529 n (%)
Atrial fibrillation | 11 (0.70) | 3 (0.20)
Heart failure | 15 (0.95) | 11 (0.72)
Lung edema | 11 (0.70) | 11 (0.72)
Pneumonia | 13 (0.82) | 9 (0.59)

Adverse Reactions in Lovenox-Treated Patients with Acute ST-Segment Elevation Myocardial Infarction

In a clinical trial in patients with acute ST-segment elevation myocardial infarction, thrombocytopenia occurred at a rate of 1.5%.

6.2 Postmarketing Experience

The following adverse reactions have been identified during postapproval use of Lovenox. Because these reactions are reported voluntarily from a population of uncertain size, it is not always possible to reliably estimate their frequency or establish a causal relationship to drug exposure.

There have been reports of epidural or spinal hematoma formation with concurrent use of Lovenox and spinal/epidural anesthesia or spinal puncture. The majority of patients had a postoperative indwelling epidural catheter placed for analgesia or received additional drugs affecting hemostasis such as NSAIDs. Many of the epidural or spinal hematomas caused neurologic injury, including long-term or permanent paralysis.

Local reactions at the injection site (e.g. nodules, inflammation, oozing), systemic allergic reactions (e.g. pruritus, urticaria, anaphylactic/anaphylactoid reactions including shock), vesiculobullous rash, cases of hypersensitivity cutaneous vasculitis, purpura, skin necrosis (occurring at either the injection site or distant from the injection site), thrombocytosis, and thrombocytopenia with thrombosis [see Warnings and Precautions (5.5)] have been reported.

Cases of hyperkalemia have been reported. Most of these reports occurred in patients who also had conditions that tend toward the development of hyperkalemia (e.g., renal dysfunction, concomitant potassium-sparing drugs, administration of potassium, hematoma in body tissues). Very rare cases of hyperlipidemia have also been reported, with one case of hyperlipidemia, with marked hypertriglyceridemia, reported in a diabetic pregnant woman; causality has not been determined.

Cases of headache, hemorrhagic anemia, eosinophilia, alopecia, hepatocellular and cholestatic liver injury have been reported.

Osteoporosis has also been reported following long-term therapy.

7 DRUG INTERACTIONS

Whenever possible, agents which may enhance the risk of hemorrhage should be discontinued prior to initiation of Lovenox therapy. These agents include medications such as: anticoagulants, platelet inhibitors including acetylsalicylic acid, salicylates, NSAIDs (including ketorolac tromethamine), dipyridamole, or sulfinpyrazone. If coadministration is essential, conduct close clinical and laboratory monitoring [see Warnings and Precautions (5.1)].

8 USE IN SPECIFIC POPULATIONS

8.1 Pregnancy

Risk Summary

Placental transfer of enoxaparin was observed in the animal studies. Human data from a retrospective cohort study, which included 693 live births, suggest that enoxaparin does not increase the risk of major developmental abnormalities (see Data). Based on animal data, Lovenox is not predicted to increase the risk of major developmental abnormalities (see Data).

Adverse outcomes in pregnancy occur regardless of the health of the mother or the use of medications. The estimated background risk of major birth defects and miscarriage for the indicated populations is unknown. In the U.S. general population, the estimated background risk of major birth defects and miscarriage in clinically recognized pregnancies is 2% to 4% and 15% to 20%, respectively.

Clinical Considerations

Pregnancy alone confers an increased risk for thromboembolism that is even higher for women with thromboembolic disease and certain high risk pregnancy conditions. While not adequately studied, pregnant women with mechanical prosthetic heart valves may be at even higher risk for thrombosis [see Warnings and Precautions (5.7) and Use in Specific Populations (8.6)]. Pregnant women with thromboembolic disease, including those with mechanical prosthetic heart valves and those with inherited or acquired thrombophilias, have an increased risk of other maternal complications and fetal loss regardless of the type of anticoagulant used.

All patients receiving anticoagulants, including pregnant women, are at risk for bleeding. Pregnant women receiving Lovenox should be carefully monitored for evidence of bleeding or excessive anticoagulation. Consideration for use of a shorter acting anticoagulant should be specifically addressed as delivery approaches [see Boxed Warning]. Hemorrhage can occur at any site and may lead to death of mother and/or fetus. Pregnant women should be apprised of the potential hazard to the fetus and the mother if Lovenox is administered during pregnancy.

It is not known if monitoring of anti-Factor Xa activity and dose adjustment (by weight or anti-Factor Xa activity) of Lovenox affect the safety and the efficacy of the drug during pregnancy.

Cases of "gasping syndrome" have occurred in premature infants when large amounts of benzyl alcohol have been administered (99–405 mg/kg/day). The multiple-dose vial of Lovenox contains 15 mg benzyl alcohol per 1 mL as a preservative [see Warnings and Precautions (5.8)].

Data

Human data

There are no adequate and well-controlled studies in pregnant women. A retrospective study reviewed the records of 604 women who used Lovenox during pregnancy. A total of 624 pregnancies resulted in 693 live births. There were 72 hemorrhagic events (11 serious) in 63 women. There were 14 cases of neonatal hemorrhage. Major congenital anomalies in live births occurred at rates (2.5%) similar to background rates.

There have been postmarketing reports of fetal death when pregnant women received Lovenox. Causality for these cases has not been determined. Insufficient data, the underlying disease, and the possibility of inadequate anticoagulation complicate the evaluation of these cases.

A clinical study using Lovenox in pregnant women with mechanical prosthetic heart valves has been conducted [see Warnings and Precautions (5.7)].

Animal data

Teratology studies have been conducted in pregnant rats and rabbits at subcutaneous doses of enoxaparin up to 15 times the recommended human dose (by comparison with 2 mg/kg as the maximum recommended daily dose). There was no evidence of teratogenic effects or fetotoxicity due to enoxaparin. Because animal reproduction studies are not always predictive of human response, this drug should be used during pregnancy only if clearly needed.

8.2 Lactation

Risk Summary

It is unknown whether Lovenox is excreted in human milk. In lactating rats, the passage of enoxaparin or its metabolites in the milk is very limited. There is no information available on the effect of enoxaparin or its metabolites on the breastfed child, or on the milk production. The developmental and health benefits of breastfeeding should be considered along with the mother's clinical need for Lovenox and any potential adverse effects on the breastfed child from Lovenox or from the underlying maternal condition.

8.4 Pediatric Use

Safety and effectiveness of Lovenox in pediatric patients have not been established.

Lovenox is not approved for use in neonates or infants.

Serious adverse reactions including fatal reactions and the "gasping syndrome" occurred in premature neonates and low-birth-weight infants in the neonatal intensive care unit who received drugs containing benzyl alcohol as a preservative. In these cases, benzyl alcohol dosages of 99 to 234 mg/kg/day produced high levels of benzyl alcohol and its metabolites in the blood and urine (blood levels of benzyl alcohol were 0.61 to 1.378 mmol/L). Additional adverse reactions included gradual neurological deterioration, seizures, intracranial hemorrhage, hematologic abnormalities, skin breakdown, hepatic and renal failure, hypotension, bradycardia, and cardiovascular collapse. Preterm, low-birth-weight infants may be more likely to develop these reactions because they may be less able to metabolize benzyl alcohol. The minimum amount of benzyl alcohol at which serious adverse reactions may occur is not known.

Lovenox multiple-dose vials contain 15 mg/mL of benzyl alcohol (at the dose of 1.5 mg/kg twice a day, benzyl alcohol exposure in patients is 0.45 mg/kg daily) [see Warnings and Precautions (5.8)].

8.5 Geriatric Use

Prevention of Deep Vein Thrombosis in Hip, Knee and Abdominal Surgery; Treatment of Deep Vein Thrombosis, Prevention of Ischemic Complications of Unstable Angina and Non–Q-Wave Myocardial Infarction

Over 2800 patients, 65 years and older, have received Lovenox in clinical trials. The efficacy of Lovenox in the geriatric (≥65 years) was similar to that seen in younger patients (<65 years). The incidence of bleeding complications was similar between geriatric and younger patients when 30 mg every 12 hours or 40 mg once a day doses of Lovenox were employed. The incidence of bleeding complications was higher in geriatric patients as compared to younger patients when Lovenox was administered at doses of 1.5 mg/kg once a day or 1 mg/kg every 12 hours. The risk of Lovenox-associated bleeding increased with age. Serious adverse events increased with age for patients receiving Lovenox. Other clinical experience (including postmarketing surveillance and literature reports) has not revealed additional differences in the safety of Lovenox between geriatric and younger patients. Careful attention to dosing intervals and concomitant medications (especially antiplatelet medications) is advised. Lovenox should be used with care in geriatric patients who may show delayed elimination of enoxaparin. Monitoring of geriatric patients with low body weight (<45 kg) and those predisposed to decreased renal function should be considered [see Warnings and Precautions (2.6) and Clinical Pharmacology (12.3)].

Treatment of Acute ST-Segment Elevation Myocardial Infarction

In the clinical study for treatment of acute ST-segment elevation myocardial infarction, there was no evidence of difference in efficacy between patients ≥75 years of age (n=1241) and patients less than 75 years of age (n=9015). Patients ≥75 years of age did not receive a 30 mg intravenous bolus prior to the normal dosage regimen and had their subcutaneous dose adjusted to 0.75 mg/kg every 12 hours [see Dosage and Administration (2.4)]. The incidence of bleeding complications was higher in patients ≥65 years of age as compared to younger patients (<65 years).

8.6 Patients with Mechanical Prosthetic Heart Valves

The use of Lovenox has not been adequately studied for thromboprophylaxis in patients with mechanical prosthetic heart valves and has not been adequately studied for long-term use in this patient population. Isolated cases of prosthetic heart valve thrombosis have been reported in patients with mechanical prosthetic heart valves who have received Lovenox for thromboprophylaxis. Some of these cases were pregnant women in whom thrombosis led to maternal and fetal deaths. Insufficient data, the underlying disease and the possibility of inadequate anticoagulation complicate the evaluation of these cases. Pregnant women with mechanical prosthetic heart valves may be at higher risk for thromboembolism [see Warnings and Precautions (5.7)].

8.7 Renal Impairment

In patients with renal impairment, there is an increase in exposure of enoxaparin sodium. All such patients should be observed carefully for signs and symptoms of bleeding. Because exposure of enoxaparin sodium is significantly increased in patients with severe renal impairment (creatinine clearance <30 mL/min), a dosage adjustment is recommended for therapeutic and prophylactic dosage ranges. No dosage adjustment is recommended in patients with creatinine clearance 30 to <50 mL/min and creatinine clearance 50 to 80 mL/min [see Dosage and Administration (2.3) and Clinical Pharmacology (12.3)]. In patients with renal failure, treatment with Lovenox has been associated with the development of hyperkalemia [see Adverse Reactions (6.2)].

8.8 Low-Weight Patients

An increase in exposure of enoxaparin sodium with prophylactic dosages (non-weight adjusted) has been observed in low-weight women (<45 kg) and low-weight men (<57 kg). Observe low-weight patients frequently for signs and symptoms of bleeding [see Clinical Pharmacology (12.3)].

8.9 Obese Patients

Obese patients are at higher risk for thromboembolism. The safety and efficacy of prophylactic doses of Lovenox in obese patients (BMI >30 kg/m^2) has not been fully determined and there is no consensus for dose adjustment. Observe these patients carefully for signs and symptoms of thromboembolism.

10 OVERDOSAGE

Accidental overdosage following administration of Lovenox may lead to hemorrhagic complications. Injected Lovenox may be largely neutralized by the slow intravenous injection of protamine sulfate (1% solution). The dose of protamine sulfate should be equal to the dose of Lovenox injected: 1 mg protamine sulfate should be administered to neutralize 1 mg Lovenox, if Lovenox was administered in the previous 8 hours. An infusion of 0.5 mg protamine per 1 mg of Lovenox may be administered if Lovenox was administered greater than 8 hours previous to the protamine administration, or if it has been determined that a second dose of protamine is required. The second infusion of 0.5 mg protamine sulfate per 1 mg of Lovenox may be administered if the aPTT measured 2 to 4 hours after the first infusion remains prolonged.

If at least 12 hours have elapsed since the last Lovenox injection, protamine administration may not be required; however, even with higher doses of protamine, the aPTT may remain more prolonged than following administration of heparin. In all cases, the anti-Factor Xa activity is never completely neutralized (maximum about 60%). Particular care should be taken to avoid overdosage with protamine sulfate. Administration of protamine sulfate can cause severe hypotensive and anaphylactoid reactions. Because fatal reactions, often resembling anaphylaxis, have been reported with protamine sulfate, it should be given only when resuscitation techniques and treatment of anaphylactic shock are readily available. For additional information consult the labeling of protamine sulfate injection products.

11 DESCRIPTION

Lovenox is a sterile aqueous solution containing enoxaparin sodium, a low molecular weight heparin. The pH of the injection is 5.5 to 7.5.

Enoxaparin sodium is obtained by alkaline depolymerization of heparin benzyl ester derived from porcine intestinal mucosa. Its structure is characterized by a 2-O-sulfo-4-enepyranosuronic acid group at the non-reducing end and a 2-N,6-O-disulfo-D-glucosamine at the reducing end of the chain. About 20% (ranging between 15% and 25%) of the enoxaparin structure contains a 1,6-anhydro derivative on the reducing end of the polysaccharide chain. The drug substance is the sodium salt. The average molecular weight is about 4500 daltons. The molecular weight distribution is:

 | <2000 daltons | ≤20%
 | 2000 to 8000 daltons | ≥68%
 | >8000 daltons | ≤18%

STRUCTURAL FORMULA

R1 = H or SO3Na and R2 = SO3Na or COCH3

R | X [X = Percent of polysaccharide chain containing 1,6-anhydro derivative on the reducing end] =15 to 25% |  | n=0 to 20
 | 100-X | H | n=1 to 21

Lovenox 100 mg/mL Concentration contains 10 mg enoxaparin sodium (approximate anti-Factor Xa activity of 1000 IU [with reference to the W.H.O. First International Low Molecular Weight Heparin Reference Standard]) per 0.1 mL Water for Injection.

Lovenox 150 mg/mL Concentration contains 15 mg enoxaparin sodium (approximate anti-Factor Xa activity of 1500 IU [with reference to the W.H.O. First International Low Molecular Weight Heparin Reference Standard]) per 0.1 mL Water for Injection.

The Lovenox prefilled syringes and graduated prefilled syringes are preservative-free and intended for use only as a single-dose injection. The multiple-dose vial contains 15 mg benzyl alcohol per 1 mL as a preservative [see Dosage and Administration (2) and How Supplied/Storage and Handling (16)].

12 CLINICAL PHARMACOLOGY

12.1 Mechanism of Action

Enoxaparin is a low molecular weight heparin which has antithrombotic properties.

12.2 Pharmacodynamics

In humans, enoxaparin given at a dose of 1.5 mg/kg subcutaneously is characterized by a higher ratio of anti-Factor Xa to anti-Factor IIa activity (mean ±SD, 14.0±3.1) (based on areas under anti-Factor activity versus time curves) compared to the ratios observed for heparin (mean ±SD, 1.22±0.13). Increases of up to 1.8 times the control values were seen in the thrombin time (TT) and the activated partial thromboplastin time (aPTT). Enoxaparin at a 1 mg/kg dose (100 mg/mL concentration), administered subcutaneously every 12 hours to patients in a large clinical trial resulted in aPTT values of 45 seconds or less in the majority of patients (n=1607). A 30 mg intravenous bolus immediately followed by a 1 mg/kg subcutaneous administration resulted in aPTT postinjection values of 50 seconds. The average aPTT prolongation value on Day 1 was about 16% higher than on Day 4.

12.3 Pharmacokinetics

Absorption

Pharmacokinetic trials were conducted using the 100 mg/mL formulation. Maximum anti-Factor Xa and anti-thrombin (anti-Factor IIa) activities occur 3 to 5 hours after subcutaneous injection of enoxaparin. Mean peak anti-Factor Xa activity was 0.16 IU/mL (1.58 mcg/mL) and 0.38 IU/mL (3.83 mcg/mL) after the 20 mg and the 40 mg clinically tested subcutaneous doses, respectively. Mean (n=46) peak anti-Factor Xa activity was 1.1 IU/mL at steady state in patients with unstable angina receiving 1 mg/kg subcutaneously every 12 hours for 14 days. Mean absolute bioavailability of enoxaparin, after 1.5 mg/kg given subcutaneously, based on anti-Factor Xa activity is approximately 100% in healthy subjects.

A 30 mg intravenous bolus immediately followed by 1 mg/kg subcutaneously every 12 hours provided initial peak anti-Factor Xa levels of 1.16 IU/mL (n=16) and average exposure corresponding to 84% of steady-state levels. Steady state is achieved on the second day of treatment.

Enoxaparin pharmacokinetics appears to be linear over the recommended dosage ranges [see Dosage and Administration (2)]. After repeated subcutaneous administration of 40 mg once daily and 1.5 mg/kg once-daily regimens in healthy volunteers, the steady state is reached on day 2 with an average exposure ratio about 15% higher than after a single dose. Steady-state enoxaparin activity levels are well predicted by single-dose pharmacokinetics. After repeated subcutaneous administration of the 1 mg/kg twice-daily regimen, the steady state is reached from day 4 with mean exposure about 65% higher than after a single dose and mean peak and trough levels of about 1.2 and 0.52 IU/mL, respectively. Based on enoxaparin sodium pharmacokinetics, this difference in steady state is expected and within the therapeutic range.

Although not studied clinically, the 150 mg/mL concentration of enoxaparin sodium is projected to result in anticoagulant activities similar to those of 100 mg/mL and 200 mg/mL concentrations at the same enoxaparin dose. When a daily 1.5 mg/kg subcutaneous injection of enoxaparin sodium was given to 25 healthy male and female subjects using a 100 mg/mL or a 200 mg/mL concentration the following pharmacokinetic profiles were obtained (see Table 13).

Table 13: Pharmacokinetic Parameters [Means ±SD at Day 5 and 90% Confidence Interval (CI) of the ratio] After 5 Days of 1.5 mg/kg Subcutaneous Once-Daily Doses of Enoxaparin Sodium Using 100 mg/mL or 200 mg/mL Concentrations
 | Concentration | Anti-Xa | Anti-IIa | Heptest | aPTT
Amax (IU/mL or Δ sec) | 100 mg/mL | 1.37 (±0.23) | 0.23 (±0.05) | 105 (±17) | 19 (±5)
Amax (IU/mL or Δ sec) | 200 mg/mL | 1.45 (±0.22) | 0.26 (±0.05) | 111 (±17) | 22 (±7)
Amax (IU/mL or Δ sec) | 90% CI | 102%–110% |  | 102%–111%
tmax [Median (range)] (h) | 100 mg/mL | 3 (2–6) | 4 (2–5) | 2.5 (2–4.5) | 3 (2–4.5)
tmax [Median (range)] (h) | 200 mg/mL | 3.5 (2–6) | 4.5 (2.5–6) | 3.3 (2–5) | 3 (2–5)
AUC (ss) (h*IU/mL or h* Δ sec) | 100 mg/mL | 14.26 (±2.93) | 1.54 (±0.61) | 1321 (±219)
AUC (ss) (h*IU/mL or h* Δ sec) | 200 mg/mL | 15.43 (±2.96) | 1.77 (±0.67) | 1401 (±227)
AUC (ss) (h*IU/mL or h* Δ sec) | 90% CI | 105%–112% |  | 103%–109%

Distribution

The volume of distribution of anti-Factor Xa activity is about 4.3 L.

Elimination

Following intravenous dosing, the total body clearance of enoxaparin is 26 mL/min. After intravenous dosing of enoxaparin labeled with the gamma-emitter, 99mTc, 40% of radioactivity and 8 to 20% of anti-Factor Xa activity were recovered in urine in 24 hours. Elimination half-life based on anti-Factor Xa activity was 4.5 hours after a single subcutaneous dose to about 7 hours after repeated dosing. Significant anti-Factor Xa activity persists in plasma for about 12 hours following a 40 mg subcutaneous once a day dose.

Following subcutaneous dosing, the apparent clearance (CL/F) of enoxaparin is approximately 15 mL/min.

Metabolism

Enoxaparin sodium is primarily metabolized in the liver by desulfation and/or depolymerization to lower molecular weight species with much reduced biological potency. Renal clearance of active fragments represents about 10% of the administered dose and total renal excretion of active and non-active fragments 40% of the dose.

Special Populations

Gender

Apparent clearance and Amax derived from anti-Factor Xa values following single subcutaneous dosing (40 mg and 60 mg) were slightly higher in males than in females. The source of the gender difference in these parameters has not been conclusively identified; however, body weight may be a contributing factor.

Geriatric

Apparent clearance and Amax derived from anti-Factor Xa values following single and multiple subcutaneous dosing in geriatric subjects were close to those observed in young subjects. Following once a day subcutaneous dosing of 40 mg enoxaparin, the Day 10 mean area under anti-Factor Xa activity versus time curve (AUC) was approximately 15% greater than the mean Day 1 AUC value [see Dosage and Administration (2.4) and Use in Specific Populations (8.5)].

Renal impairment

A linear relationship between anti-Factor Xa plasma clearance and creatinine clearance at steady state has been observed, which indicates decreased clearance of enoxaparin sodium in patients with reduced renal function. Anti-Factor Xa exposure represented by AUC, at steady state, is marginally increased in patients with creatinine clearance 50 to 80 mL/min and patients with creatinine clearance 30 to <50 mL/min after repeated subcutaneous 40 mg once-daily doses. In patients with severe renal impairment (creatinine clearance <30 mL/min), the AUC at steady state is significantly increased on average by 65% after repeated subcutaneous 40 mg once-daily doses [see Dosage and Administration (2.3) and Use in Specific Populations (8.7)].

Hemodialysis

In a single study, elimination rate appeared similar but AUC was two-fold higher than control population, after a single 0.25 or 0.5 mg/kg intravenous dose.

Hepatic impairment

Studies with Lovenox in patients with hepatic impairment have not been conducted and the impact of hepatic impairment on the exposure to enoxaparin is unknown.

Weight

After repeated subcutaneous 1.5 mg/kg once-daily dosing, mean AUC of anti-Factor Xa activity is marginally higher at steady state in obese healthy volunteers (BMI 30–48 kg/m^2) compared to non-obese control subjects, while Amax is not increased.

When non–weight-adjusted dosing was administered, it was found after a single-subcutaneous 40 mg dose, that anti-Factor Xa exposure is 52% higher in low-weight women (<45 kg) and 27% higher in low-weight men (<57 kg) when compared to normal weight control subjects [see Use in Specific Populations (8.8)].

Pharmacokinetic Interaction

No pharmacokinetic interaction was observed between Lovenox and thrombolytics when administered concomitantly.

13 NONCLINICAL TOXICOLOGY

13.1 Carcinogenesis, Mutagenesis, Impairment of Fertility

No long-term studies in animals have been performed to evaluate the carcinogenic potential of enoxaparin. Enoxaparin was not mutagenic in in vitro tests, including the Ames test, mouse lymphoma cell forward mutation test, and human lymphocyte chromosomal aberration test, and the in vivo rat bone marrow chromosomal aberration test. Enoxaparin was found to have no effect on fertility or reproductive performance of male and female rats at subcutaneous doses up to 20 mg/kg/day or 141 mg/m^2/day. The maximum human dose in clinical trials was 2.0 mg/kg/day or 78 mg/m^2/day (for an average body weight of 70 kg, height of 170 cm, and body surface area of 1.8 m^2).

13.2 Animal Toxicology and/or Pharmacology

A single subcutaneous dose of 46.4 mg/kg enoxaparin was lethal to rats. The symptoms of acute toxicity were ataxia, decreased motility, dyspnea, cyanosis, and coma.

13.3 Reproductive and Developmental Toxicology

Teratology studies have been conducted in pregnant rats and rabbits at subcutaneous doses of enoxaparin up to 30 mg/kg/day corresponding to 211 mg/m^2/day and 410 mg/m^2/day in rats and rabbits respectively. There was no evidence of teratogenic effects or fetotoxicity due to enoxaparin.

14 CLINICAL STUDIES

14.1 Prophylaxis of Deep Vein Thrombosis following Abdominal Surgery in Patients at Risk for Thromboembolic Complications

Abdominal surgery patients at risk include those who are over 40 years of age, obese, undergoing surgery under general anesthesia lasting longer than 30 minutes or who have additional risk factors such as malignancy or a history of deep vein thrombosis (DVT) or pulmonary embolism (PE).

In a double-blind, parallel group study of patients undergoing elective cancer surgery of the gastrointestinal, urological, or gynecological tract, a total of 1116 patients were enrolled in the study, and 1115 patients were treated. Patients ranged in age from 32 to 97 years (mean age 67 years) with 52.7% men and 47.3% women. Patients were 98% Caucasian, 1.1% Black, 0.4% Asian and 0.4% others. Lovenox 40 mg subcutaneously, administered once a day, beginning 2 hours prior to surgery and continuing for a maximum of 12 days after surgery, was comparable to heparin 5000 U every 8 hours subcutaneously in reducing the risk of DVT. The efficacy data are provided below (see Table 14).

Table 14: Efficacy of Lovenox in the Prophylaxis of Deep Vein Thrombosis following Abdominal Surgery
 | Dosing Regimen
Indication | Lovenox 40 mg daily subcutaneously n (%) | Heparin 5000 U q8h subcutaneously n (%)
All Treated Abdominal Surgery Patients | 555 (100) | 560 (100)
Treatment Failures
Total VTE [VTE = Venous thromboembolic events which included DVT, PE, and death considered to be thromboembolic in origin] (%) | 56 (10.1) (95% CI [CI = Confidence Interval] : 8 to 13) | 63 (11.3) (95% CI: 9 to 14)
DVT Only (%) | 54 (9.7) (95% CI: 7 to 12) | 61 (10.9) (95% CI: 8 to 13)

In a second double-blind, parallel group study, Lovenox 40 mg subcutaneously once a day was compared to heparin 5000 U every 8 hours subcutaneously in patients undergoing colorectal surgery (one-third with cancer). A total of 1347 patients were randomized in the study and all patients were treated. Patients ranged in age from 18 to 92 years (mean age 50.1 years) with 54.2% men and 45.8% women. Treatment was initiated approximately 2 hours prior to surgery and continued for approximately 7 to 10 days after surgery. The efficacy data are provided below (see Table 15).

Table 15: Efficacy of Lovenox in the Prophylaxis of Deep Vein Thrombosis following Colorectal Surgery
 | Dosing Regimen
Indication | Lovenox 40 mg daily subcutaneously n (%) | Heparin 5000 U q8h subcutaneously n (%)
All Treated Colorectal Surgery Patients | 673 (100) | 674 (100)
Treatment Failures
Total VTE [VTE = Venous thromboembolic events which included DVT, PE, and death considered to be thromboembolic in origin] (%) | 48 (7.1) (95% CI [CI = Confidence Interval] : 5 to 9) | 45 (6.7) (95% CI: 5 to 9)
DVT Only (%) | 47 (7.0) (95% CI: 5 to 9) | 44 (6.5) (95% CI: 5 to 8)

14.2 Prophylaxis of Deep Vein Thrombosis following Hip or Knee Replacement Surgery

Lovenox has been shown to reduce the risk of postoperative deep vein thrombosis (DVT) following hip or knee replacement surgery.

In a double-blind study, Lovenox 30 mg every 12 hours subcutaneously was compared to placebo in patients with hip replacement. A total of 100 patients were randomized in the study and all patients were treated. Patients ranged in age from 41 to 84 years (mean age 67.1 years) with 45% men and 55% women. After hemostasis was established, treatment was initiated 12 to 24 hours after surgery and was continued for 10 to 14 days after surgery. The efficacy data are provided below (see Table 16).

Table 16: Efficacy of Lovenox in the Prophylaxis of Deep Vein Thrombosis following Hip Replacement Surgery
 | Dosing Regimen
Indication | Lovenox 30 mg q12h subcutaneously n (%) | Placebo q12h subcutaneously n (%)
All Treated Hip Replacement Patients | 50 (100) | 50 (100)
Treatment Failures
Total DVT (%) | 5 (10) [p value versus placebo = 0.0002] | 23 (46)
Proximal DVT (%) | 1 (2) [p value versus placebo = 0.0134] | 11 (22)

A double-blind, multicenter study compared three dosing regimens of Lovenox in patients with hip replacement. A total of 572 patients were randomized in the study and 568 patients were treated. Patients ranged in age from 31 to 88 years (mean age 64.7 years) with 63% men and 37% women. Patients were 93% Caucasian, 6% Black, <1% Asian, and 1% others. Treatment was initiated within two days after surgery and was continued for 7 to 11 days after surgery. The efficacy data are provided below (see Table 17).

Table 17: Efficacy of Lovenox in the Prophylaxis of Deep Vein Thrombosis following Hip Replacement Surgery
 | Dosing Regimen
Indication | 10 mg daily subcutaneously n (%) | 30 mg q12h subcutaneously n (%) | 40 mg daily subcutaneously n (%)
All Treated Hip Replacement Patients | 161 (100) | 208 (100) | 199 (100)
Treatment Failures
Total DVT (%) | 40 (25) | 22 (11) [p value versus Lovenox 10 mg once a day = 0.0008] | 27 (14)
Proximal DVT (%) | 17 (11) | 8 (4) [p value versus Lovenox 10 mg once a day = 0.0168] | 9 (5)

There was no significant difference between the 30 mg every 12 hours and 40 mg once a day regimens. In a double-blind study, Lovenox 30 mg every 12 hours subcutaneously was compared to placebo in patients undergoing knee replacement surgery. A total of 132 patients were randomized in the study and 131 patients were treated, of which 99 had total knee replacement and 32 had either unicompartmental knee replacement or tibial osteotomy. The 99 patients with total knee replacement ranged in age from 42 to 85 years (mean age 70.2 years) with 36.4% men and 63.6% women. After hemostasis was established, treatment was initiated 12 to 24 hours after surgery and was continued up to 15 days after surgery. The incidence of proximal and total DVT after surgery was significantly lower for Lovenox compared to placebo. The efficacy data are provided below (see Table 18).

Table 18: Efficacy of Lovenox in the Prophylaxis of Deep Vein Thrombosis following Total Knee Replacement Surgery
 | Dosing Regimen
Indication | Lovenox 30 mg q12h subcutaneously n (%) | Placebo q12h subcutaneously n (%)
All Treated Total Knee Replacement Patients | 47 (100) | 52 (100)
Treatment Failures
Total DVT (%) | 5 (11) [p value versus placebo = 0.0001] (95% CI [CI = Confidence Interval] : 1 to 21) | 32 (62) (95% CI: 47 to 76)
Proximal DVT (%) | 0 (0) [p value versus placebo = 0.013] (95% Upper CL [CL = Confidence Limit] : 5) | 7 (13) (95% CI: 3 to 24)

Additionally, in an open-label, parallel group, randomized clinical study, Lovenox 30 mg every 12 hours subcutaneously in patients undergoing elective knee replacement surgery was compared to heparin 5000 U every 8 hours subcutaneously. A total of 453 patients were randomized in the study and all were treated. Patients ranged in age from 38 to 90 years (mean age 68.5 years) with 43.7% men and 56.3% women. Patients were 92.5% Caucasian, 5.3% Black, and 0.6% others. Treatment was initiated after surgery and continued up to 14 days. The incidence of deep vein thrombosis was lower for Lovenox compared to heparin.

Extended Prophylaxis of Deep Vein Thrombosis following Hip Replacement Surgery: In a study of extended prophylaxis for patients undergoing hip replacement surgery, patients were treated, while hospitalized, with Lovenox 40 mg subcutaneously, initiated up to 12 hours prior to surgery for the prophylaxis of postoperative DVT. At the end of the peri-operative period, all patients underwent bilateral venography. In a double-blind design, those patients with no venous thromboembolic disease were randomized to a post-discharge regimen of either Lovenox 40 mg (n=90) once a day subcutaneously or to placebo (n=89) for 3 weeks. A total of 179 patients were randomized in the double-blind phase of the study and all patients were treated. Patients ranged in age from 47 to 87 years (mean age 69.4 years) with 57% men and 43% women. In this population of patients, the incidence of DVT during extended prophylaxis was significantly lower for Lovenox compared to placebo. The efficacy data are provided below (see Table 19).

Table 19: Efficacy of Lovenox in the Extended Prophylaxis of Deep Vein Thrombosis following Hip Replacement Surgery
 | Post-discharge Dosing Regimen
Indication (Post Discharge) | Lovenox 40 mg daily subcutaneously n (%) | Placebo daily subcutaneously n (%)
All Treated Extended Prophylaxis Patients | 90 (100) | 89 (100)
Treatment Failures
Total DVT (%) | 6 (7) [p value versus placebo = 0.008] (95% CI [CI= Confidence Interval] : 3 to 14) | 18 (20) (95% CI: 12 to 30)
Proximal DVT (%) | 5 (6) [p value versus placebo = 0.537] (95% CI: 2 to 13) | 7 (8) (95% CI: 3 to 16)

In a second study, patients undergoing hip replacement surgery were treated, while hospitalized, with Lovenox 40 mg subcutaneously, initiated up to 12 hours prior to surgery. All patients were examined for clinical signs and symptoms of venous thromboembolic (VTE) disease. In a double-blind design, patients without clinical signs and symptoms of VTE disease were randomized to a post-discharge regimen of either Lovenox 40 mg (n=131) once a day subcutaneously or to placebo (n=131) for 3 weeks. A total of 262 patients were randomized in the study double-blind phase and all patients were treated. Patients ranged in age from 44 to 87 years (mean age 68.5 years) with 43.1% men and 56.9% women. Similar to the first study the incidence of DVT during extended prophylaxis was significantly lower for Lovenox compared to placebo, with a statistically significant difference in both total DVT (Lovenox 21 [16%] versus placebo 45 [34%]; p=0.001) and proximal DVT (Lovenox 8 [6%] versus placebo 28 [21%]; p=<0.001).

14.3 Prophylaxis of Deep Vein Thrombosis in Medical Patients with Severely Restricted Mobility during Acute Illness

In a double blind multicenter, parallel group study, Lovenox 20 mg or 40 mg once a day subcutaneously was compared to placebo in the prophylaxis of deep vein thrombosis (DVT) in medical patients with severely restricted mobility during acute illness (defined as walking distance of <10 meters for ≤3 days). This study included patients with heart failure (NYHA Class III or IV); acute respiratory failure or complicated chronic respiratory insufficiency (not requiring ventilatory support): acute infection (excluding septic shock); or acute rheumatic disorder (acute lumbar or sciatic pain, vertebral compression [due to osteoporosis or tumor], acute arthritic episodes of the lower extremities). A total of 1102 patients were enrolled in the study, and 1073 patients were treated. Patients ranged in age from 40 to 97 years (mean age 73 years) with equal proportions of men and women. Treatment continued for a maximum of 14 days (median duration 7 days). When given at a dose of 40 mg once a day subcutaneously, Lovenox significantly reduced the incidence of DVT as compared to placebo. The efficacy data are provided below (see Table 20).

Table 20: Efficacy of Lovenox in the Prophylaxis of Deep Vein Thrombosis in Medical Patients with Severely Restricted Mobility during Acute Illness
 | Dosing Regimen
 | Lovenox 20 mg daily subcutaneously | Lovenox 40 mg daily subcutaneously | Placebo
Indication | n (%) | n (%) | n (%)
All Treated Medical Patients during Acute Illness | 351 (100) | 360 (100) | 362 (100)
Treatment Failure [Treatment failures during therapy, between Days 1 and 14]
Total VTE [VTE = Venous thromboembolic events which included DVT, PE, and death considered to be thromboembolic in origin] (%) | 43 (12.3) | 16 (4.4) | 43 (11.9)
Total DVT (%) | 43 (12.3) (95% CI [CI = Confidence Interval] : 8.8 to 15.7) | 16 (4.4) (95% CI: 2.3 to 6.6) | 41 (11.3) (95% CI: 8.1 to 14.6)
Proximal DVT (%) | 13 (3.7) | 5 (1.4) | 14 (3.9)

At approximately 3 months following enrollment, the incidence of venous thromboembolism remained lower in the Lovenox 40 mg treatment group versus the placebo treatment group.

14.4 Treatment of Deep Vein Thrombosis with or without Pulmonary Embolism

In a multicenter, parallel group study, 900 patients with acute lower extremity deep vein thrombosis (DVT) with or without pulmonary embolism (PE) were randomized to an inpatient (hospital) treatment of either (i) Lovenox 1.5 mg/kg once a day subcutaneously, (ii) Lovenox 1 mg/kg every 12 hours subcutaneously, or (iii) heparin intravenous bolus (5000 IU) followed by a continuous infusion (administered to achieve an aPTT of 55 to 85 seconds). A total of 900 patients were randomized in the study and all patients were treated. Patients ranged in age from 18 to 92 years (mean age 60.7 years) with 54.7% men and 45.3% women. All patients also received warfarin sodium (dose adjusted according to PT to achieve an International Normalization Ratio [INR] of 2.0 to 3.0), commencing within 72 hours of initiation of Lovenox or standard heparin therapy, and continuing for 90 days. Lovenox or standard heparin therapy was administered for a minimum of 5 days and until the targeted warfarin sodium INR was achieved. Both Lovenox regimens were equivalent to standard heparin therapy in reducing the risk of recurrent venous thromboembolism (DVT and/or PE). The efficacy data are provided below (see Table 21).

Table 21: Efficacy of Lovenox in Treatment of Deep Vein Thrombosis with or without Pulmonary Embolism
 | Dosing Regimen [All patients were also treated with warfarin sodium commencing within 72 hours of Lovenox or standard heparin therapy.]
 | Lovenox 1.5 mg/kg daily subcutaneously | Lovenox 1 mg/kg q12h subcutaneously | Heparin aPTT Adjusted Intravenous Therapy
Indication | n (%) | n (%) | n (%)
All Treated DVT Patients with or without PE | 298 (100) | 312 (100) | 290 (100)
Patient Outcome
Total VTE [VTE = venous thromboembolic event (DVT and/or PE)] (%) | 13 (4.4) [The 95% Confidence Intervals for the treatment differences for total VTE were: Lovenox once a day versus heparin (-3.0 to 3.5) Lovenox every 12 hours versus heparin (-4.2 to 1.7)] | 9 (2.9) | 12 (4.1)
DVT Only (%) | 11 (3.7) | 7 (2.2) | 8 (2.8)
Proximal DVT (%) | 9 (3.0) | 6 (1.9) | 7 (2.4)
PE (%) | 2 (0.7) | 2 (0.6) | 4 (1.4)

Similarly, in a multicenter, open-label, parallel group study, patients with acute proximal DVT were randomized to Lovenox or heparin. Patients who could not receive outpatient therapy were excluded from entering the study. Outpatient exclusion criteria included the following: inability to receive outpatient heparin therapy because of associated comorbid conditions or potential for non-compliance and inability to attend follow-up visits as an outpatient because of geographic inaccessibility. Eligible patients could be treated in the hospital, but ONLY Lovenox patients were permitted to go home on therapy (72%). A total of 501 patients were randomized in the study and all patients were treated. Patients ranged in age from 19 to 96 years (mean age 57.8 years) with 60.5% men and 39.5% women. Patients were randomized to either Lovenox 1 mg/kg every 12 hours subcutaneously or heparin intravenous bolus (5000 IU) followed by a continuous infusion administered to achieve an aPTT of 60 to 85 seconds (in-patient treatment). All patients also received warfarin sodium as described in the previous study. Lovenox or standard heparin therapy was administered for a minimum of 5 days. Lovenox was equivalent to standard heparin therapy in reducing the risk of recurrent venous thromboembolism. The efficacy data are provided below (see Table 22).

Table 22: Efficacy of Lovenox in Treatment of Deep Vein Thrombosis
 | Dosing Regimen [All patients were also treated with warfarin sodium commencing on the evening of the second day of Lovenox or standard heparin therapy.]
 | Lovenox 1 mg/kg q12h subcutaneously | Heparin aPTT Adjusted Intravenous Therapy
Indication | n (%) | n (%)
All Treated DVT Patients | 247 (100) | 254 (100)
Patient Outcome
Total VTE [VTE = venous thromboembolic event (deep vein thrombosis [DVT] and/or pulmonary embolism [PE]).] (%) | 13 (5.3) [The 95% Confidence Intervals for the treatment difference for total VTE was: Lovenox versus heparin (-5.6 to 2.7).] | 17 (6.7)
DVT Only (%) | 11 (4.5) | 14 (5.5)
Proximal DVT (%) | 10 (4.0) | 12 (4.7)
PE (%) | 2 (0.8) | 3 (1.2)

14.5 Prophylaxis of Ischemic Complications in Unstable Angina and Non–Q-Wave Myocardial Infarction

In a multicenter, double-blind, parallel group study, patients who recently experienced unstable angina or non–Q-wave myocardial infarction were randomized to either Lovenox 1 mg/kg every 12 hours subcutaneously or heparin intravenous bolus (5000 U) followed by a continuous infusion (adjusted to achieve an aPTT of 55 to 85 seconds). A total of 3171 patients were enrolled in the study, and 3107 patients were treated. Patients ranged in age from 25 to 94 years (median age 64 years), with 33.4% of patients female and 66.6% male. Race was distributed as follows: 89.8% Caucasian, 4.8% Black, 2.0% Asian, and 3.5% other. All patients were also treated with aspirin 100 to 325 mg per day. Treatment was initiated within 24 hours of the event and continued until clinical stabilization, revascularization procedures, or hospital discharge, with a maximal duration of 8 days of therapy. The combined incidence of the triple endpoint of death, myocardial infarction, or recurrent angina was lower for Lovenox compared with heparin therapy at 14 days after initiation of treatment. The lower incidence of the triple endpoint was sustained up to 30 days after initiation of treatment. These results were observed in an analysis of both all-randomized and all-treated patients. The efficacy data are provided below (see Table 23).

Table 23: Efficacy of Lovenox in the Prophylaxis of Ischemic Complications in Unstable Angina and Non–Q-Wave Myocardial Infarction (combined endpoint of death, myocardial infarction, or recurrent angina)
 | Dosing Regimen [All patients were also treated with aspirin 100 to 325 mg per day.]
 | Lovenox 1 mg/kg q12h subcutaneously | Heparin aPTT Adjusted Intravenous Therapy | Reduction (%) | p Value
Indication | n (%) | n (%)
All Treated Unstable Angina and Non–Q-Wave MI Patients | 1578 (100) | 1529 (100) | – | –
Time point [Evaluation time points are after initiation of treatment. Therapy continued for up to 8 days (median duration of 2.6 days).]
48 Hours | 96 (6.1) | 112 (7.3) | 1.2 | 0.120
14 Days | 261 (16.5) | 303 (19.8) | 3.3 | 0.017
30 Days | 313 (19.8) | 358 (23.4) | 3.6 | 0.014

The combined incidence of death or myocardial infarction at all time points was lower for Lovenox compared to standard heparin therapy, but did not achieve statistical significance. The efficacy data are provided below (see Table 24).

Table 24: Efficacy of Lovenox in the Prophylaxis of Ischemic Complications in Unstable Angina and Non–Q-Wave Myocardial Infarction (Combined endpoint of death or myocardial infarction)
 | Dosing Regimen [All patients were also treated with aspirin 100 to 325 mg per day.]
 | Lovenox 1 mg/kg q12h subcutaneously | Heparin aPTT Adjusted Intravenous Therapy | Reduction (%) | p Value
Indication | n (%) | n (%)
All Treated Unstable Angina and Non–Q-Wave MI Patients | 1578 (100) | 1529 (100)
Time point [Evaluation time points are after initiation of treatment. Therapy continued for up to 8 days (median duration of 2.6 days).]
48 Hours | 16 (1.0) | 20 (1.3) | 0.3 | 0.126
14 Days | 76 (4.8) | 93 (6.1) | 1.3 | 0.115
30 Days | 96 (6.1) | 118 (7.7) | 1.6 | 0.069

In a survey one year following treatment, with information available for 92% of enrolled patients, the combined incidence of death, myocardial infarction, or recurrent angina remained lower for Lovenox versus heparin (32.0% vs 35.7%).

Urgent revascularization procedures were performed less frequently in the Lovenox group as compared to the heparin group, 6.3% compared to 8.2% at 30 days (p=0.047).

14.6 Treatment of Acute ST-Segment Elevation Myocardial Infarction

In a multicenter, double-blind, double-dummy, parallel-group study, patients with acute ST-segment elevation myocardial infarction (STEMI) who were to be hospitalized within 6 hours of onset and were eligible to receive fibrinolytic therapy were randomized in a 1:1 ratio to receive either Lovenox or unfractionated heparin.

Study medication was initiated between 15 minutes before and 30 minutes after the initiation of fibrinolytic therapy. Unfractionated heparin was administered beginning with an intravenous bolus of 60 U/kg (maximum 4000 U) and followed with an infusion of 12 U/kg per hour (initial maximum 1000 U per hour) that was adjusted to maintain an aPTT of 1.5 to 2 times the control value. The intravenous infusion was to be given for at least 48 hours. The Lovenox dosing strategy was adjusted according to the patient's age and renal function. For patients younger than 75 years of age, Lovenox was given as a single 30 mg intravenous bolus plus a 1 mg/kg subcutaneous dose followed by a subcutaneous injection of 1 mg/kg every 12 hours. For patients at least 75 years of age, the intravenous bolus was not given and the subcutaneous dose was reduced to 0.75 mg/kg every 12 hours. For patients with severe renal insufficiency (estimated creatinine clearance of less than 30 mL per minute), the dose was to be modified to 1 mg/kg every 24 hours. The subcutaneous injections of Lovenox were given until hospital discharge or for a maximum of eight days (whichever came first). The mean treatment duration for Lovenox was 6.6 days. The mean treatment duration of unfractionated heparin was 54 hours.

When percutaneous coronary intervention was performed during study medication period, patients received antithrombotic support with blinded study drug. For patients on Lovenox, the PCI was to be performed on Lovenox (no switch) using the regimen established in previous studies, i.e. no additional dosing, if the last subcutaneous administration was less than 8 hours before balloon inflation, intravenous bolus of 0.3 mg/kg Lovenox if the last subcutaneous administration was more than 8 hours before balloon inflation.

All patients were treated with aspirin for a minimum of 30 days. Eighty percent of patients received a fibrin-specific agent (19% tenecteplase, 5% reteplase and 55% alteplase) and 20% received streptokinase.

Among 20,479 patients in the ITT population, the mean age was 60 years, and 76% were male. Racial distribution was: 87% Caucasian, 9.8% Asian, 0.2% Black, and 2.8% other. Medical history included previous MI (13%), hypertension (44%), diabetes (15%) and angiographic evidence of CAD (5%). Concomitant medication included aspirin (95%), beta-blockers (86%), ACE inhibitors (78%), statins (70%) and clopidogrel (27%). The MI at entry was anterior in 43%, non-anterior in 56%, and both in 1%.

The primary efficacy endpoint was the composite of death from any cause or myocardial re-infarction in the first 30 days after randomization. Total follow-up was one year.

The rate of the primary efficacy endpoint (death or myocardial re-infarction) was 9.9% in the Lovenox group, and 12% in the unfractionated heparin group, a 17% reduction in the relative risk, (P=0.000003) (see Table 25).

Table 25: Efficacy of Lovenox in the Treatment of Acute ST-Segment Elevation Myocardial Infarction
 | Lovenox (N=10,256) | UFH (N=10,223) | Relative Risk (95% CI) | P Value
Outcome at 48 hours | n (%) | n (%)
Death or Myocardial Re-infarction | 478 (4.7) | 531 (5.2) | 0.90 (0.80 to 1.01) | 0.08
Death | 383 (3.7) | 390 (3.8) | 0.98 (0.85 to 1.12) | 0.76
Myocardial Re-infarction | 102 (1.0) | 156 (1.5) | 0.65 (0.51 to 0.84) | <0.001
Urgent Revascularization | 74 (0.7) | 96 (0.9) | 0.77 (0.57 to 1.04) | 0.09
Death or Myocardial Re-infarction or Urgent Revascularization | 548 (5.3) | 622 (6.1) | 0.88 (0.79 to 0.98) | 0.02
Outcome at 8 Days
Death or Myocardial Re-infarction | 740 (7.2) | 954 (9.3) | 0.77 (0.71 to 0.85) | <0.001
Death | 559 (5.5) | 605 (5.9) | 0.92 (0.82 to 1.03) | 0.15
Myocardial Re-infarction | 204 (2.0) | 379 (3.7) | 0.54 (0.45 to 0.63) | <0.001
Urgent Revascularization | 145 (1.4) | 247 (2.4) | 0.59 (0.48 to 0.72) | <0.001
Death or Myocardial Re-infarction or Urgent Revascularization | 874 (8.5) | 1181 (11.6) | 0.74 (0.68 to 0.80) | <0.001
Outcome at 30 Days
Primary efficacy endpoint (Death or Myocardial Re-infarction) | 1017 (9.9) | 1223 (12.0) | 0.83 (0.77 to 0.90) | 0.000003
Death | 708 (6.9) | 765 (7.5) | 0.92 (0.84 to 1.02) | 0.11
Myocardial Re-infarction | 352 (3.4) | 508 (5.0) | 0.69 (0.60 to 0.79) | <0.001
Urgent Revascularization | 213 (2.1) | 286 (2.8) | 0.74 (0.62 to 0.88) | <0.001
Death or Myocardial Re-infarction or Urgent Revascularization | 1199 (11.7) | 1479 (14.5) | 0.81 (0.75 to 0.87) | <0.001
Note: Urgent revascularization denotes episodes of recurrent myocardial ischemia (without infarction) leading to the clinical decision to perform coronary revascularization during the same hospitalization. CI denotes confidence intervals.

The beneficial effect of Lovenox on the primary endpoint was consistent across key subgroups including age, gender, infarct location, history of diabetes, history of prior myocardial infarction, fibrinolytic agent administered, and time to treatment with study drug (see Figure 1); however, it is necessary to interpret such subgroup analyses with caution.

Figure 1: Relative Risks of and Absolute Event Rates for the Primary Endpoint at 30 Days in Various Subgroups [The primary efficacy endpoint was the composite of death from any cause or myocardial re-infarction in the first 30 days. The overall treatment effect of Lovenox as compared to the unfractionated heparin (UFH) is shown at the bottom of the figure. For each subgroup, the circle is proportional to the number and represents the point estimate of the treatment effect and the horizontal lines represent the 95% confidence intervals. Fibrin-specific fibrinolytic agents included alteplase, tenecteplase, and reteplase. Time to treatment indicates the time from the onset of symptoms to the administration of study drug (median: 3.2 hours).]

The beneficial effect of Lovenox on the primary endpoint observed during the first 30 days was maintained over a 12 month follow-up period (see Figure 2).

Figure 2: Kaplan-Meier Plot – Death or Myocardial Re-infarction at 30 Days – ITT Population

There is a trend in favor of Lovenox during the first 48 hours, but most of the treatment difference is attributed to a step increase in the event rate in the UFH group at 48 hours (seen in Figure 2), an effect that is more striking when comparing the event rates just prior to and just subsequent to actual times of discontinuation. These results provide evidence that UFH was effective and that it would be better if used longer than 48 hours. There is a similar increase in endpoint event rate when Lovenox was discontinued, suggesting that it too was discontinued too soon in this study.

The rates of major hemorrhages (defined as requiring 5 or more units of blood for transfusion, or 15% drop in hematocrit or clinically overt bleeding, including intracranial hemorrhage) at 30 days were 2.1% in the Lovenox group and 1.4% in the unfractionated heparin group. The rates of intracranial hemorrhage at 30 days were 0.8% in the Lovenox group and 0.7% in the unfractionated heparin group. The 30-day rate of the composite endpoint of death, myocardial re-infarction or ICH (a measure of net clinical benefit) was significantly lower in the Lovenox group (10.1%) as compared to the heparin group (12.2%).

16 HOW SUPPLIED/STORAGE AND HANDLING

Lovenox is available in two concentrations (see Tables 26 and 27).

Table 26: 100 mg/mL Concentration
Dosage Unit/Strength [Strength represents the number of milligrams of enoxaparin sodium in Water for Injection. Lovenox 30 and 40 mg prefilled syringes, and 60, 80, and 100 mg graduated prefilled syringes each contain 10 mg enoxaparin sodium per 0.1 mL Water for Injection.] | Anti-Xa Activity [Approximate anti-Factor Xa activity based on reference to the W.H.O. First International Low Molecular Weight Heparin Reference Standard.] | Package Size (per carton) | Label Color | NDC # 0075-
Single-Dose Prefilled Syringes [Each Lovenox prefilled syringe is for single, one-time use only and is affixed with a 27 gauge × 1/2-inch needle.]
30 mg/0.3 mL | 3000 IU | 10 syringes | Medium Blue | 0624-30
40 mg/0.4 mL | 4000 IU | 10 syringes | Yellow | 0620-40
Single-Dose Graduated Prefilled Syringes
60 mg/0.6 mL | 6000 IU | 10 syringes | Orange | 0621-60
80 mg/0.8 mL | 8000 IU | 10 syringes | Brown | 0622-80
100 mg/1 mL | 10,000 IU | 10 syringes | Black | 0623-00
Multiple-Dose Vial [Each Lovenox multiple-dose vial contains 15 mg benzyl alcohol per 1 mL as a preservative.]
300 mg/3 mL | 30,000 IU | 1 vial | Red | 0626-03

Table 27: 150 mg/mL Concentration
Dosage Unit/Strength [Strength represents the number of milligrams of enoxaparin sodium in Water for Injection. Lovenox 120 and 150 mg graduated prefilled syringes contain 15 mg enoxaparin sodium per 0.1 mL Water for Injection.] | Anti-Xa Activity [Approximate anti-Factor Xa activity based on reference to the W.H.O. First International Low Molecular Weight Heparin Reference Standard.] | Package Size (per carton) | Syringe Label Color | NDC # 0075-
Single-Dose Graduated Prefilled Syringes [Each Lovenox graduated prefilled syringe is for single, one-time use only and is affixed with a 27 gauge × 1/2-inch needle.]
120 mg/0.8 mL | 12,000 IU | 10 syringes | Purple | 2912-01
150 mg/1 mL | 15,000 IU | 10 syringes | Navy Blue | 2915-01

STORAGE AND HANDLING

Store at 25°C (77°F); excursions permitted to 15°C–30°C (59°F–86°F) [see USP Controlled Room Temperature]. Store in the original carton or packaging until ready to use.

Do not store the multiple-dose vials for more than 28 days after the first use.

17 PATIENT COUNSELING INFORMATION

Advise the patient to read the FDA-approved patient labeling (Instructions for Use).

If patients have had neuraxial anesthesia or spinal puncture, and particularly, if they are taking concomitant NSAIDs, platelet inhibitors, or other anticoagulants, advise them to watch for signs and symptoms of spinal or epidural hematoma, such as tingling, numbness (especially in the lower limbs) and muscular weakness. Instruct the patient to seek immediate medical attention if any of these symptoms occur.

Inform patients:

- of the instructions for injecting Lovenox if they continue Lovenox therapy after discharge from the hospital.
- that it may take them longer than usual to stop bleeding.
- that they may bruise and/or bleed more easily when they use Lovenox.
- that they should report any unusual bleeding, bruising, or signs of thrombocytopenia (such as a rash of dark red spots under the skin) to their physician [see Warnings and Precautions (5.1, 5.5)].
- that risks are associated with the use of benzyl alcohol, a preservative in Lovenox multiple-dose vials, in neonates, infants, and pregnant women.
- to tell their physicians and dentists they are taking Lovenox and/or any other product known to affect bleeding before any surgery is scheduled and before any new drug is taken [see Warnings and Precautions (5.1, 5.3)].
- to tell their physicians and dentists of all medications they are taking, including those obtained without a prescription, such as aspirin or other NSAIDs [see Drug Interactions (7)].

sanofi-aventis U.S. LLC
Morristown, NJ 07960
A SANOFI COMPANY

©2025 sanofi-aventis U.S. LLC

INSTRUCTIONS FOR USE

LOVENOX® (low-vuh-naaks)
(enoxaparin sodium injection)
for subcutaneous use

Single-dose prefilled syringe

This Instructions for Use contains information on how to prepare and inject Lovenox prefilled syringe.

Read this Instructions for Use before using the Lovenox prefilled syringe and each time you get a new prescription. There may be new information. Do not inject yourself or someone else until you have been shown how to inject Lovenox. Your healthcare provider can show you or your caregiver how to prepare and inject a dose of Lovenox. Call your healthcare provider if you have any questions.

Important information:

- Your healthcare provider will tell you the prescribed dose that you should take and how often you will need to inject Lovenox. If your dose is based on your body weight, your dose of Lovenox might be less than what is in the prefilled syringe.
- Lovenox is injected as a subcutaneous (under the skin) injection only. Do not inject Lovenox into muscle.
- Do not use the Lovenox prefilled syringe if the needle cap is missing or not securely attached.
- Do not remove the needle cap until just before you give the injection.
- Do not touch the syringe plunger rod until you are ready to inject. Do not pull back on the plunger rod at any time.

- Do not get rid of any air bubble(s) in the Lovenox prefilled syringe. This can lead to a loss of the medicine.
- To avoid bruising, do not rub the injection site after you have injected yourself.
- To protect from needle-stick injuries, each prefilled syringe has a safety system that covers the needle after injection.
- Throw away (dispose of) the used Lovenox prefilled syringe and needle cap right away after use, even if there is medicine left in the prefilled syringe. See "Step 13: Dispose of used Lovenox prefilled syringes and needle caps" below.
- Lovenox is for one time use only. Do not reuse a Lovenox prefilled syringe.

Storing Lovenox prefilled syringes:

- Store Lovenox prefilled syringes at 77°F (25°C).
- Store Lovenox prefilled syringes in the original carton or packaging until ready to use.
- Keep Lovenox and all medicines out of the reach of children.

Parts of Lovenox prefilled syringe:

Preparing to inject Lovenox:

Step 1: Gather the following supplies for your injection (see Figure A):

- 1 Lovenox prefilled syringe
- 1 alcohol wipe [Items not included.]
- 1 cotton ball or gauze
- a small adhesive bandage, if needed
- a sharps disposal container (see Step 13)

Figure A

Step 2: Wash your hands well with soap and water.

Step 3: Preparing a dose of Lovenox

Take the prefilled syringe out of the package.

Open the packaging by peeling the lid at the arrow as directed.

Take the prefilled syringe out of the plastic container by holding the middle of the syringe body (see Figure B).

- Do not remove the prefilled syringe by pulling on the plunger rod or the needle cap as this may damage the syringe.
- Do not pull off the needle cap until you are ready to inject.
- Do not use the Lovenox prefilled syringe if it has been dropped on a hard surface or damaged.

Figure B

Step 4: Check the Lovenox prefilled syringe

- When you receive your Lovenox syringes, always check to see that:
  - you have the correct medicine and dose.
  - the expiration date on the prefilled syringe has not passed (see Figure C).
- Do not use the Lovenox prefilled syringe if the expiration date has passed.

Figure C

Step 5: Check the medicine

- Look at the medicine inside the Lovenox prefilled syringe:
  - The liquid should be clear and colorless to pale yellow (see Figure D).
  - Note: You may see air bubble(s), this is normal. Do not try to remove any air bubbles.
- Do not use the Lovenox prefilled syringe if the liquid is discolored or cloudy, or if it contains visible flakes or particles.

Figure D

Step 6: Choose your injection site

- You can inject into either the right or left side of your stomach area (abdomen), at least 2 inches away from your belly button and out towards your side (see Figure E).
- You should alternate between the left or right side of your stomach each time you give yourself an injection.
- Do not inject into skin that has bruises or scars.
- Do not inject through clothes.

Figure E

Step 7: Clean the injection site

Clean the injection site with an alcohol wipe (see Figure F).

Let your skin dry before injecting.

Figure F

Step 8: Remove the needle cap

Hold the prefilled syringe in the middle of the body with the needle pointing away from you. Remove the needle cap by pulling it straight off the syringe (see Figure G).

- Do not twist the needle cap to avoid bending the needle.
- Do not put the needle cap back on.
- Do not touch the needle.

Figure G

Step 9: Injecting a dose that is less than the full amount in the prefilled syringe. If your prescribed dose is the same as the amount in the prefilled syringe, go to Step 10.

If your dose is based on your bodyweight, your healthcare provider may prescribe less than the full amount in the syringe. You will have to get rid of (discard) some of the medicine from the prefilled syringe before you inject Lovenox.

To measure your prescribed dose, hold the prefilled syringe with the needle pointing down. Carefully watch the numbers on the syringe as you push the plunger down until the amount left in the syringe is the same as your prescribed dose. The tip of the plunger should line up with the number for your prescribed dose (see Figure H).

Figure H

Step 10: Injecting Lovenox

Hold the prefilled syringe like a pencil in your hand with the needle pointing down. With your other hand, pinch the cleaned stomach (abdomen) area between your forefinger and thumb to make a fold in the skin (see Figure I). Make sure you hold the skin fold during the entire injection.

Figure I

Insert the full length of the needle straight into the skin fold at about a 90° angle (see Figure J).

Figure J

Push the plunger rod down slowly and steadily with your thumb until the Lovenox prefilled syringe is empty (see Figure K).

Figure K

Step 11: Remove the needle

Remove the needle from the injection site by pulling it straight out while keeping your fingers on the plunger rod (see Figure L).

- Do not put the needle cap back on.
- Do not rub your skin after the injection.

Figure L

Step 12: Activate the safety system

Point the needle away from yourself and other people, and firmly push the plunger rod again to activate the safety system. The protective sleeve will automatically come down and cover the needle. You will hear a "click" when the protective sleeve is released (see Figure M).

- You will feel some resistance. This is normal. Keep pushing until you hear the "click."
- The safety system can only be activated after the syringe has been emptied.
- Only activate the safety system after you have removed the needle from your skin.
- Activation of the safety system may cause a small amount of liquid to leak out of the syringe.
  Activate the system while facing the syringe away from yourself and other people.

Figure M

Step 13: Dispose of used Lovenox prefilled syringes and needle caps

Put the used Lovenox prefilled syringe and needle cap in an FDA-cleared sharps disposal container right away after use (see Figure N). Do not dispose of Lovenox prefilled syringes or needle caps in your household trash.

If you do not have an FDA-cleared sharps disposal container, you may use a household container that is:

- made of a heavy-duty plastic,
- can be closed with a tight-fitting, puncture-resistant lid, without sharps being able to come out,
- upright and stable during use,
- leak-resistant, and
- properly labeled to warn of hazardous waste inside the container.

When your sharps disposal container is almost full, you will need to follow your community guidelines for the right way to dispose of your sharps disposal container. There may be state or local laws about how you should throw away used needles, syringes, and prefilled syringes. For more information about safe sharps disposal, and for specific information about sharps disposal in the state that you live in, go to the FDA's website at http://www.fda.gov/safesharpsdisposal.

Figure N

sanofi-aventis U.S. LLC
Morristown, NJ 07960
A SANOFI COMPANY

©2025 sanofi-aventis U.S. LLC

This Instructions for Use has been approved by the U.S. Food and Drug Administration.
Issued: May 2025

PRINCIPAL DISPLAY PANEL - 30 mg/0.3 mL Syringe Carton

NDC 0075-0624-30

LOVENOX®
(enoxaparin sodium injection)

30mg/0.3mL

Rx ONLY

SINGLE DOSE SYRINGES WITH AUTOMATIC SAFETY DEVICE
FOR SUBCUTANEOUS INJECTION

Ten 0.3mL Syringes

SANOFI

PRINCIPAL DISPLAY PANEL - 40 mg/0.4 mL Syringe Carton

NDC 0075-0620-40
Rx only

LOVENOX®
(enoxaparin sodium) injection

40 mg/0.4 mL

For Subcutaneous Use

Ten 0.4 mL single-dose syringes with automatic safety device

sanofi

PRINCIPAL DISPLAY PANEL - 60 mg/0.6 mL Syringe Carton

NDC 0075-0621-60
Rx only

LOVENOX®
(enoxaparin sodium) injection

60 mg/0.6 mL

For Subcutaneous Use

Ten 0.6 mL single-dose syringes with automatic safety device

sanofi

PRINCIPAL DISPLAY PANEL - 80 mg/0.8 mL Syringe Carton

NDC 0075-0622-80
Rx only

LOVENOX®
(enoxaparin sodium) injection

80 mg/0.8 mL

For Subcutaneous Use

Ten 0.8 mL single-dose syringes with automatic safety device

sanofi

PRINCIPAL DISPLAY PANEL - 100 mg/1 mL Syringe Carton

NDC 0075-0623-00
Rx only

LOVENOX®
(enoxaparin sodium) injection

100 mg/1 mL

For Subcutaneous Use

Ten 1 mL single-dose syringes with automatic safety device

sanofi

PRINCIPAL DISPLAY PANEL - 300 mg/3 mL Vial Carton

NDC 0075-0626-03
Rx only

LOVENOX®
(enoxaparin sodium) injection

300 mg/3 mL
(100 mg/1 mL)

For Subcutaneous or
Intravenous Use

One 3 mL multiple-dose vial

sanofi

PRINCIPAL DISPLAY PANEL - 120 mg/0.8 mL Syringe Carton

NDC 0075-2912-01
Rx only

LOVENOX®
(enoxaparin sodium) injection

120 mg/0.8 mL

For Subcutaneous Use

Ten 0.8 mL single-dose syringes with automatic safety device

sanofi

PRINCIPAL DISPLAY PANEL - 150 mg/1 mL Syringe Carton

NDC 0075-2915-01
Rx only

LOVENOX®
(enoxaparin sodium) injection

150 mg/1 mL

For Subcutaneous Use

Ten 1 mL single-dose syringes with automatic safety device

sanofi